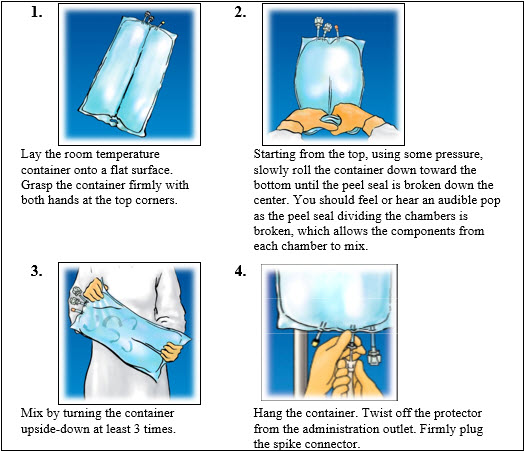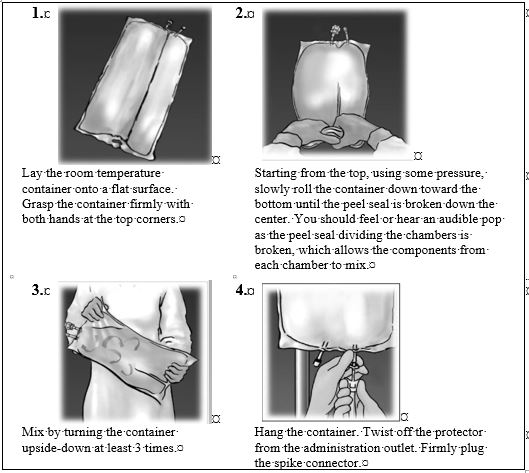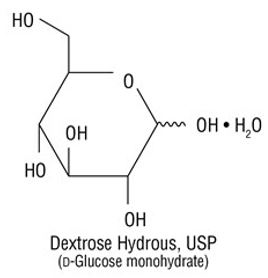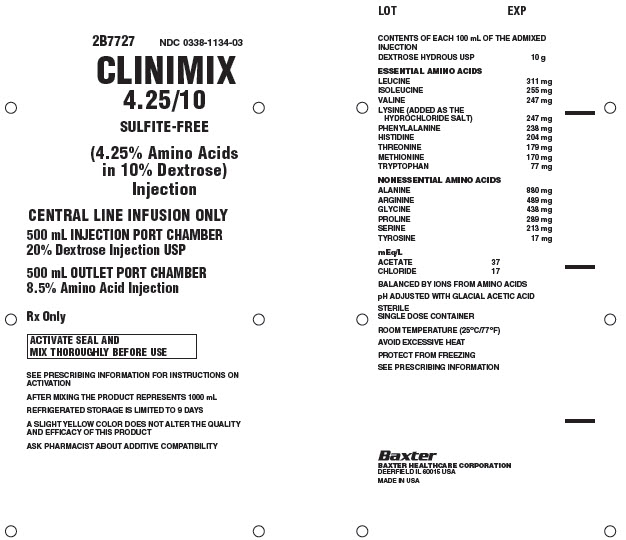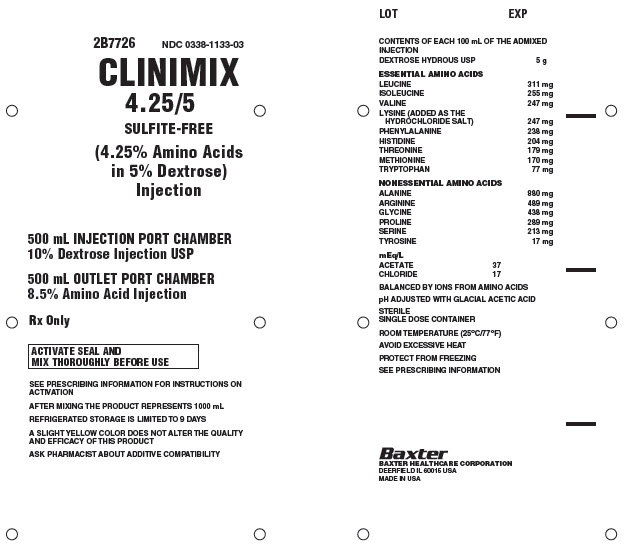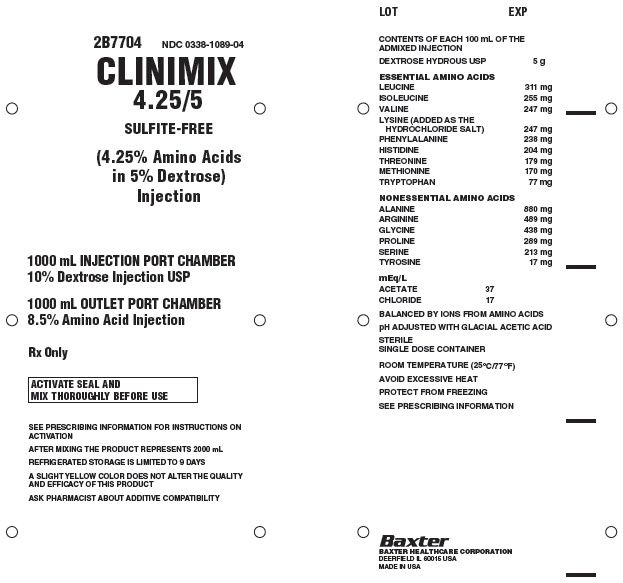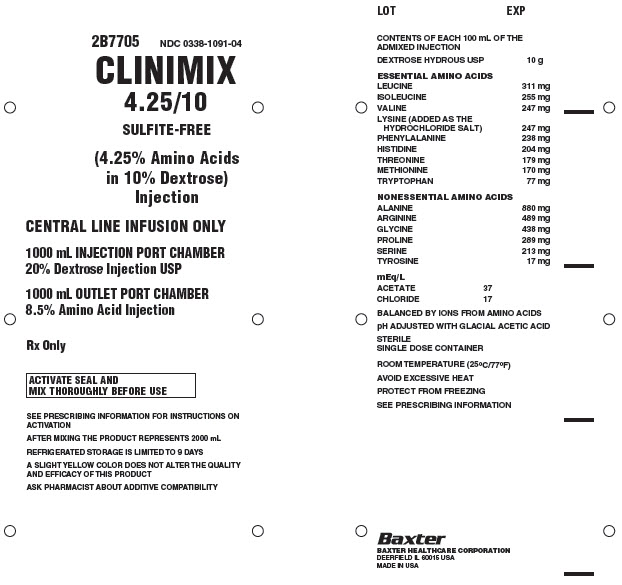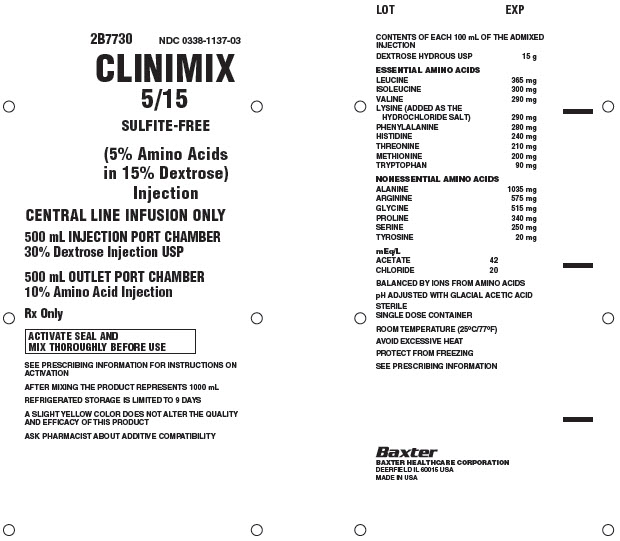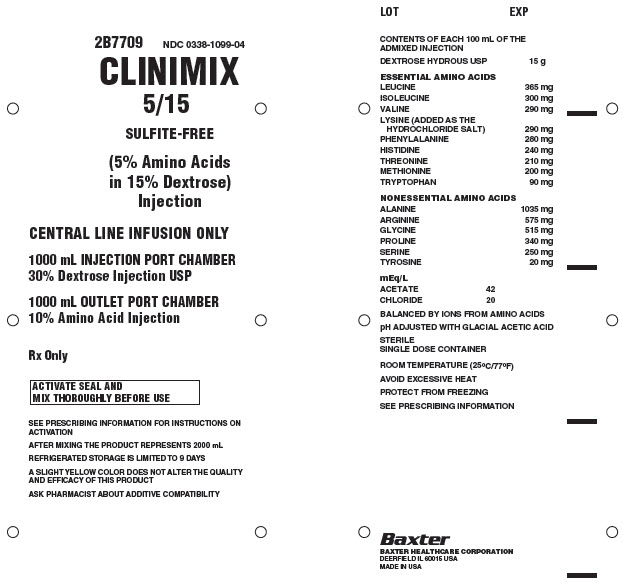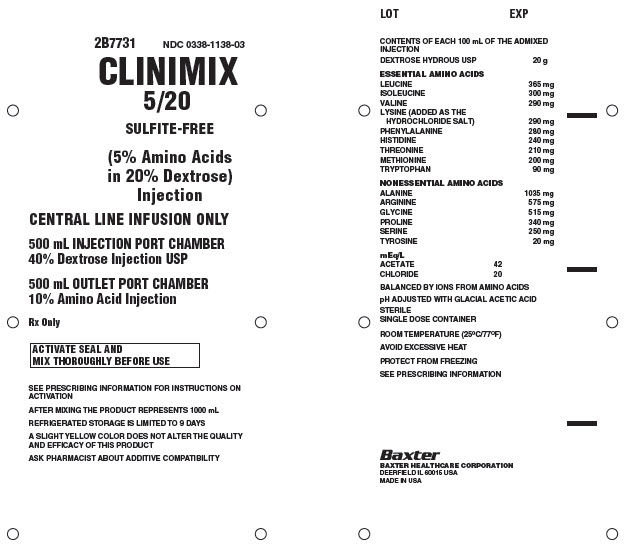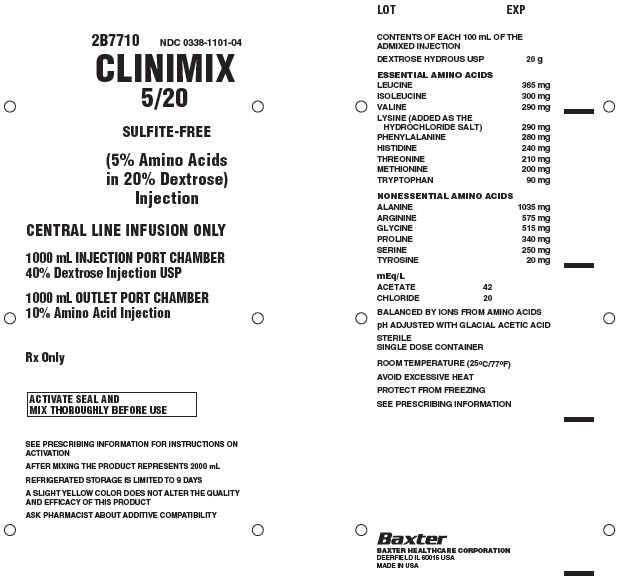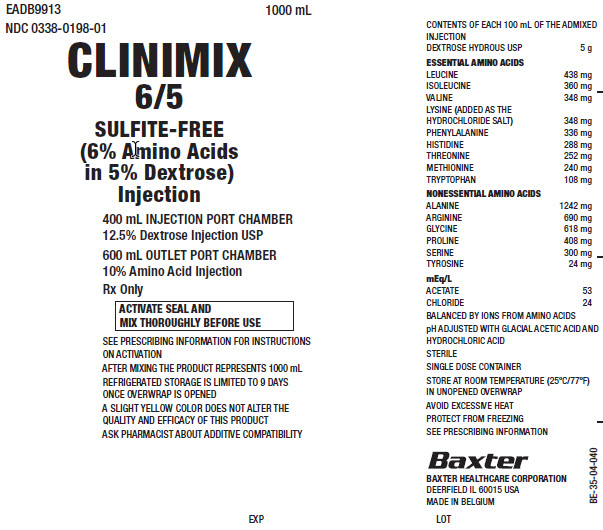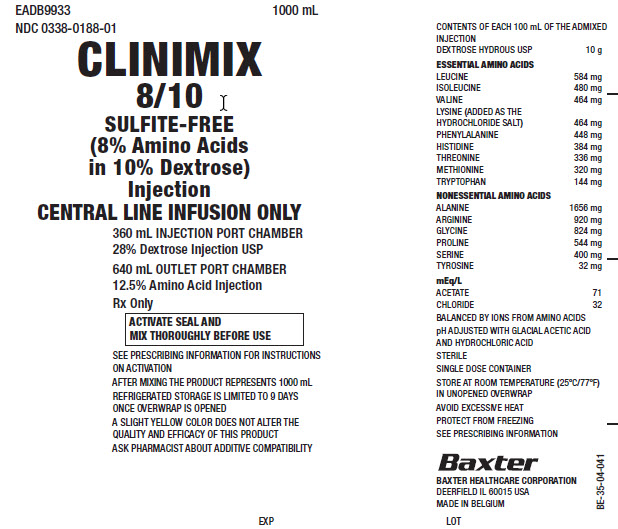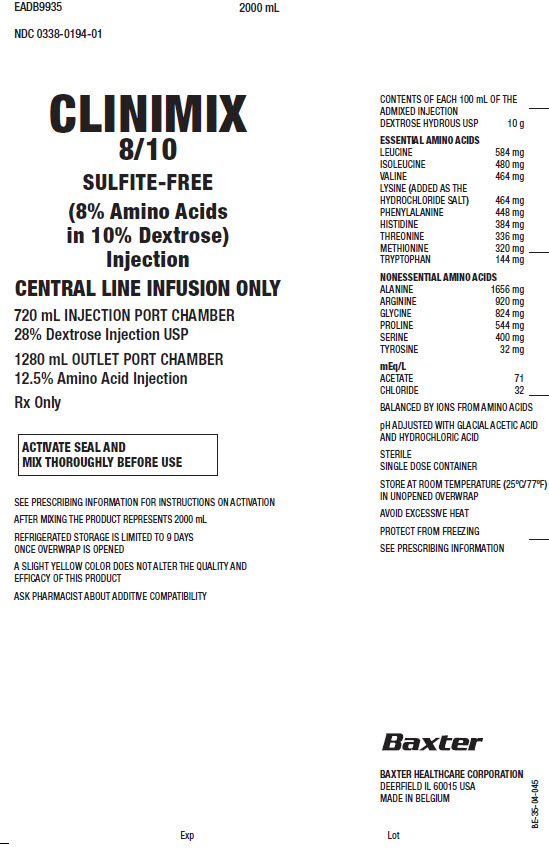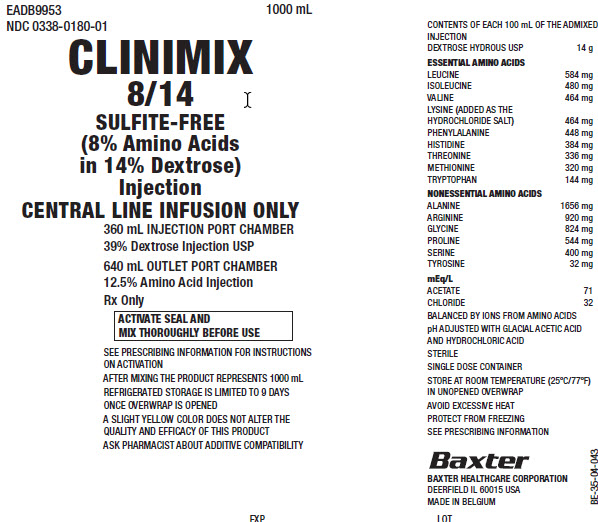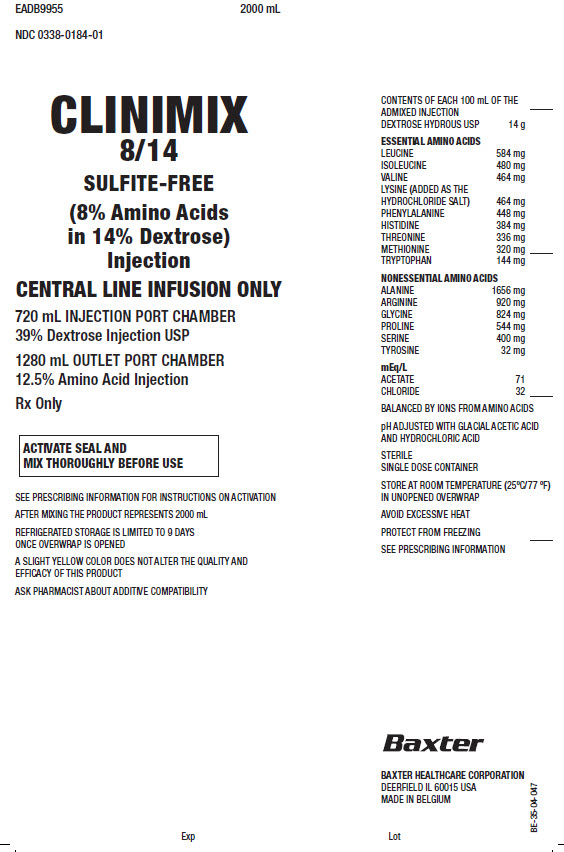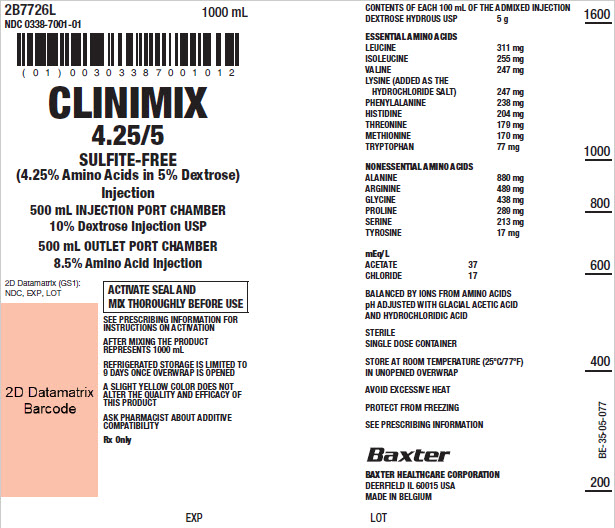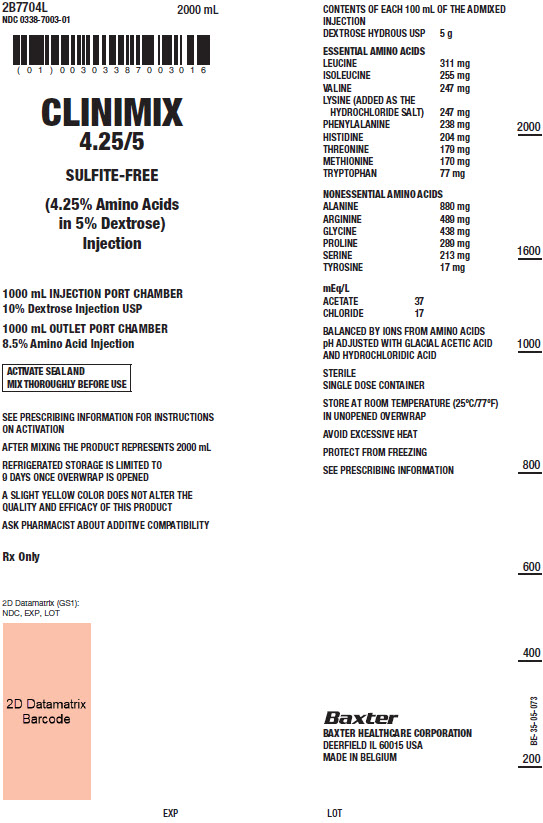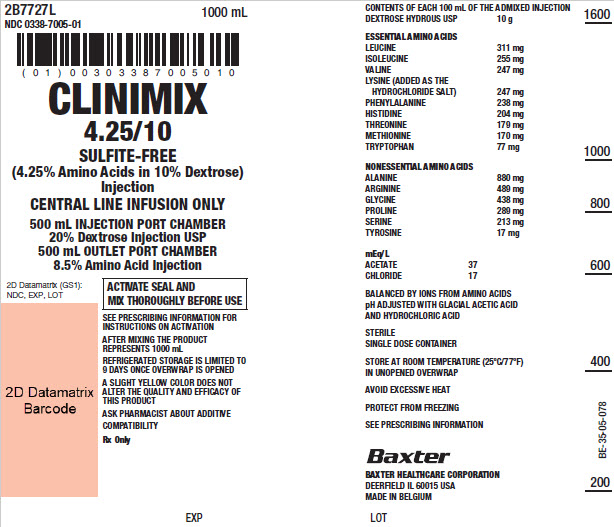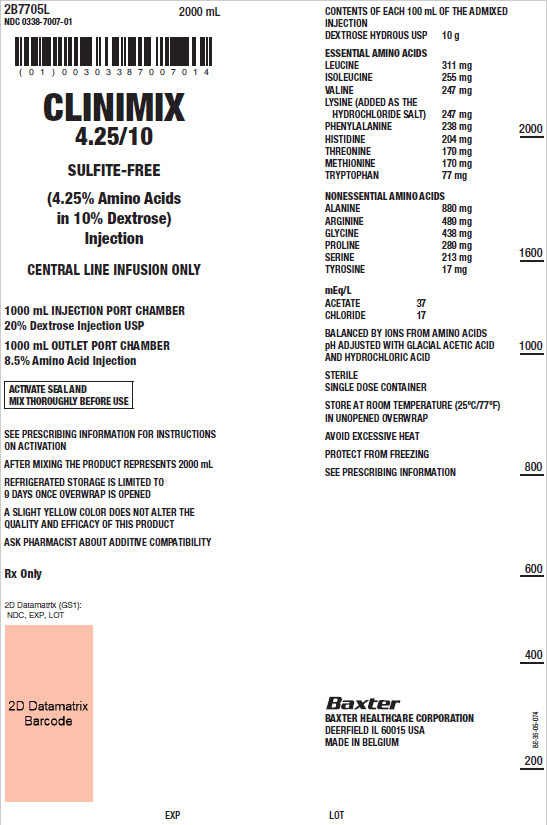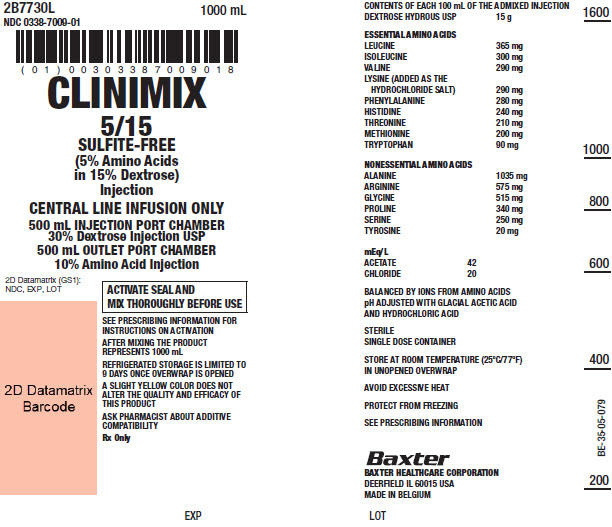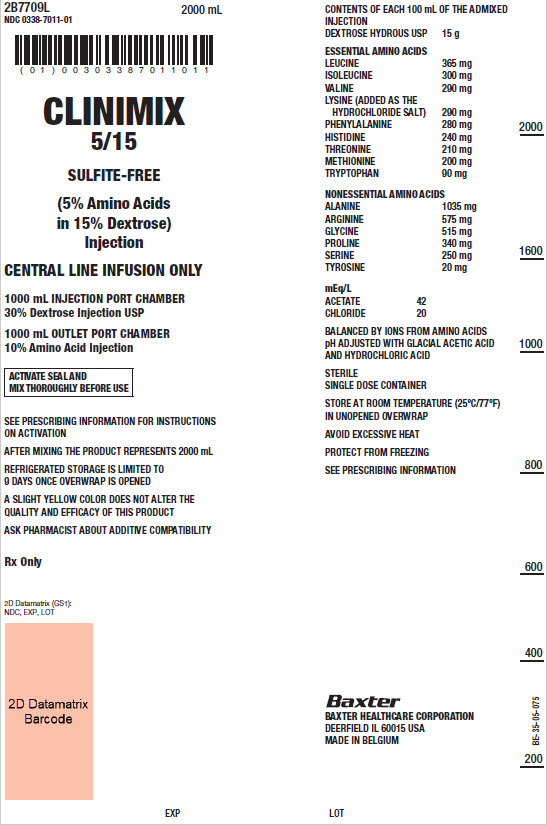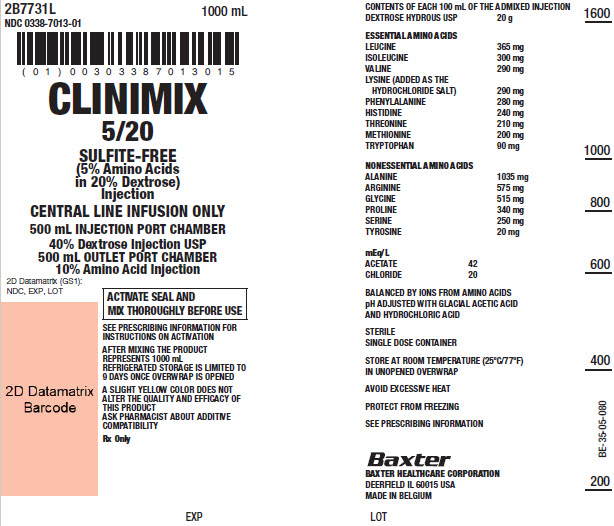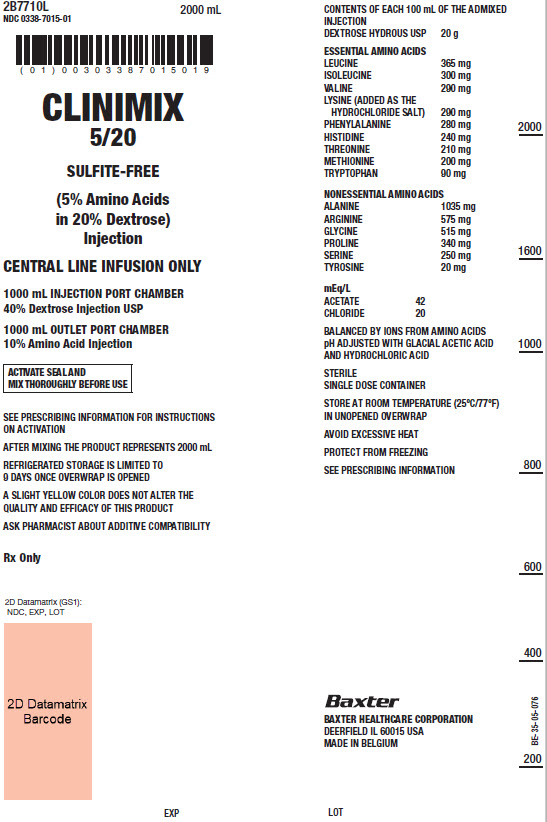 DRUG LABEL: CLINIMIX
NDC: 0338-1133 | Form: INJECTION
Manufacturer: Baxter Healthcare Corporation
Category: prescription | Type: HUMAN PRESCRIPTION DRUG LABEL
Date: 20210413

ACTIVE INGREDIENTS: LEUCINE 311 mg/100 mL; PHENYLALANINE 238 mg/100 mL; LYSINE 247 mg/100 mL; METHIONINE 170 mg/100 mL; ISOLEUCINE 255 mg/100 mL; VALINE 247 mg/100 mL; HISTIDINE 204 mg/100 mL; THREONINE 179 mg/100 mL; TRYPTOPHAN 77 mg/100 mL; ALANINE 880 mg/100 mL; GLYCINE 438 mg/100 mL; ARGININE 489 mg/100 mL; PROLINE 289 mg/100 mL; SERINE 213 mg/100 mL; TYROSINE 17 mg/100 mL; DEXTROSE 5 g/100 mL
INACTIVE INGREDIENTS: ACETIC ACID; WATER; NITROGEN

HIGHLIGHTS OF PRESCRIBING INFORMATION

These highlights do not include all the information needed to use CLINIMIX safely and effectively. See full prescribing information for CLINIMIX.
CLINIMIX (amino acids in dextrose) injection, for intravenous use
Initial U.S. Approval: 1997

RECENT MAJOR CHANGES

Dosage and Administration, Instructions for Use (2.3, 2.7) 04/2021
  Warnings and Precautions (5.5) 04/2021
  Dosage and Administration (2.1, 2.3, 2.4, 2.6, 2.8) 09/2020

1 INDICATIONS AND USAGE

CLINIMIX is indicated as a source of calories and protein for patients requiring parenteral nutrition when oral or enteral nutrition is not possible, insufficient, or contraindicated. CLINIMIX may be used to treat negative nitrogen balance in patients. (1)

2 DOSAGE AND ADMINISTRATION

See full prescribing information for information on preparation, administration, instructions for use, dosing considerations, including the recommended dosage in adults and pediatrics, and dosage modifications in patients with kidney disease. (2.1, 2.2, 2.3, 2.4, 2.5, 2.6, 2.7, 2.8)

3 DOSAGE FORMS AND STRENGTHS

CLINIMIX injection is available in multiple strengths. See full prescribing information for detailed description of each formulation. (3, 11)

4 CONTRAINDICATIONS

- Known hypersensitivity to one or more amino acids or dextrose. (4)
- Inborn errors of amino acid metabolism. (4)
- Patients with pulmonary edema or acidosis due to low cardiac output. (4)

5 WARNINGS AND PRECAUTIONS

- Pulmonary Embolism due to Pulmonary Vascular Precipitates: if signs of pulmonary distress occur, stop the infusion and initiate a medical evaluation. (5.1)
- Hypersensitivity Reactions: monitor for signs and symptoms and discontinue infusion if reactions occur. (5.2)
- Risk of Infections, Refeeding Complications, and Hyperglycemia or Hyperosmolar Hyperglycemic State: monitor for signs and symptoms; monitor laboratory parameters. (5.3, 5.4, 5.5)
- Vein Damage and Thrombosis: solutions with osmolarity of ≥ 900 mOsm/L must be infused through a central catheter. (2.2, 5.6)
- Hepatobiliary Disorders: monitor liver function parameters and ammonia levels. (5.7)
- Aluminum Toxicity: increased risk in patients with impaired kidney function, including preterm infants. (5.8, 8.4)
- Parenteral Nutrition Associated Liver Disease: increased risk in patients who receive parenteral nutrition for extended periods of time, especially preterm infants; monitor liver function tests, if abnormalities occur consider discontinuation or dosage reduction. (5.9, 8.4)
- Electrolyte Imbalance and Fluid Overload: patients with cardiac insufficiency or kidney disease may require adjustment of fluid, protein and electrolyte content. (5.10, 8.4)

6 ADVERSE REACTIONS

Adverse reactions include diuresis, extravasation, glycosuria, hyperglycemia, and hyperosmolar coma. (6)

To report SUSPECTED ADVERSE REACTIONS, contact Baxter Healthcare Corporation at 1-866-888-2472 or FDA at 1-800-FDA-1088 or www.fda.gov/medwatch

8 USE IN SPECIFIC POPULATIONS

Pediatric Use: increased risk of hypoglycemia/hyperglycemia: monitor serum glucose concentrations. (8.4)

FULL PRESCRIBING INFORMATION

1 INDICATIONS AND USAGE

CLINIMIX is indicated as a source of calories and protein for patients requiring parenteral nutrition when oral or enteral nutrition is not possible, insufficient, or contraindicated. CLINIMIX may be used to treat negative nitrogen balance in patients.

2 DOSAGE AND ADMINISTRATION

2.1 Preparation Prior to Administration

- CLINIMIX is available in a three port container configuration and a two port container configuration.
  - Three Port Container: the ports consist of one medication port, one additive port and one outlet port. Additives can be introduced to the container through the medication port and lipids through the additive port on the three port container.
  - Two Port Container: the ports consist of one medication port and one outlet port. Additives, including lipids, can be introduced to the container through the medication port on the two port container.
- Tear protective overwrap at slit and remove solution container. Small amounts of moisture may be found on the solution container from water permeating from inside the container. The amount of permeated water is insufficient to affect the solution significantly. If larger amounts of water are found, the container should be checked for tears or leaks.
- Inspect the container prior to activation. Some opacity of the plastic due to moisture absorption during the sterilization process may be observed. This is normal and does not affect the solution quality or safety. The opacity will diminish gradually. Evaluate the following:
  - If the outlet or additive port protectors are damaged, detached, or not present, discard container as solution path sterility may be impaired.
  - Check to ensure seal between chambers is intact, solutions are contained in separate chambers, and the content of the individual chambers is clear, colorless or slightly yellow. Discard if the seal is broken or if the solution is bright yellow or yellowish brown.
  - Check for minute leaks by separately squeezing each chamber. If external leaks or leakage between the chambers are found, discard solution as sterility or stability may be impaired.
- Lipids and/or additives can be introduced to the container after opening seal between chambers. Because additives may be incompatible, evaluate all additions to the plastic container for compatibility. Activate chambers of container prior to introduction of additives. Mix thoroughly when additives have been introduced. Supplemental medication may be added with a 19 to 22 gauge needle through the medication port.
- Calcium and phosphate ratios must be considered. Excess addition of calcium and phosphate, especially in the form of mineral salts, may result in the formation of calcium phosphate precipitates [see Warnings and Precautions (5.1)].
- Inspect the container to ensure precipitates have not formed during the mixing or addition of additives. A slight yellow color does not alter the quality and efficacy of this product. If lipid has been added, ensure the emulsion has not separated. Separation of the emulsion can be visibly identified by a yellowish streaking or the accumulation of yellowish droplets in the mixed emulsion. Discard the admixture if any of the above are observed.

2.2 Important Administration Instructions

- Set the vent to the closed position on a vented intravenous administration set to prevent air embolism.
- Use a dedicated line without any connections to avoid air embolism.
- CLINIMIX is for intravenous infusion only into a central or peripheral vein. The choice of a central or peripheral venous route should depend on the osmolarity of the final infusate. Solutions with osmolarity of 900 mOsm/L or greater must be infused through a central catheter [see Warnings and Precautions (5.6)].
  - For central vein infusion only: CLINIMIX 4.25/10, 5/15, 5/20, 8/10, 8/14
  - For central or peripheral vein infusion: CLINIMIX 4.25/5, 6/5
- The solution should be inspected for precipitates before admixing, after admixing, and again before administration.
- Use a 0.22 micron filter for administration of CLINIMIX. If a lipid is also administered, use a 1.2 micron filter.
- If lipid emulsion is added, do not use administration sets and lines that contain di-2-ethylhexyl phthalate (DEHP). Administration sets that contain polyvinyl chloride (PVC) components have DEHP as a plasticizer.

2.3 Instructions for Use

1. Open by tearing protective overwrap at slit and remove solution container. The two port container includes an oxygen-absorbing sachet. Discard the oxygen-absorbing sachet after removal from the overwrap.
2. To proceed with activation, the container should be at room temperature. Lay the room temperature container onto a flat surface. Grasp the container firmly on each side of the top of the container (Figure 1).
3. Starting from the top, using some pressure, slowly roll the container to open seal between chambers as shown in Figure 2. Do not pull or rip the seal apart. The seal must be completely opened towards the port side of the container. The upper section of the seal towards the hanger side can remain unbroken.
4. Mix the contents thoroughly by inverting the container upside down to ensure a homogenous admixture (Figure 3).
5. Once the container is mixed, check for leaks.
6. Make additions (if prescribed).
Because additives may be incompatible, evaluate all additions to the container for compatibility and stability of the resulting preparation. Consult with pharmacist, if available. Questions about compatibility may be directed to Baxter. If it is deemed advisable to introduce additives, use aseptic technique. For information on adding lipid emulsions see Dosage and Administration (2.4).
  a. Prepare medication port.
  b. Using syringe with 19 to 22 gauge needle, puncture resealable medication port and inject.
  c. Mix solution and medication thoroughly (Figure 3). For high density medication (high specific gravity), such as potassium chloride, squeeze ports while ports are upright and mix thoroughly.
7. Inspect final solution for discoloration and particulate matter. Check for leaks.
8. Spike and hang container.
  a. Suspend container from eyelet support.
  b. Twist off protector from outlet port at bottom of container (Figure 4).
  c. Attach administration set. Refer to complete directions accompanying set.

For single dose only. Discard unused portion.

Figures 1-4 (Three Port Container):

Figures 1-4 (Two Port Container):

Instructions on Storage

Storage After Removal of Overwrap:

Once removed from the protective overwrap, mixed (peel seal activated) or unmixed (peel seal intact) CLINIMIX solutions may be stored under refrigeration for up to 9 days.

Storage Once any Additive is Added:

Use promptly after mixing. Any storage with additives should be under refrigeration and limited to a brief period of time, less than 24 hours. After removal from refrigeration, use promptly and complete the infusion within 24 hours. Any remaining mixture must be discarded.

Protect the activated parenteral nutrition solution from light.

2.4 Preparation and Addition of Lipid Emulsion

Three Port Container

1. Prior to adding lipid emulsion, mix amino acid and dextrose injection as shown in Figures 1-3.
2. Prepare lipid emulsion transfer set following instructions provided.
3. Attach transfer set to lipid emulsion container using aseptic technique.
4. Twist off protector on the additive port of the container.
5. Attach the transfer set to the exposed additive port.
6. Open clamp on transfer set.
7. After completing transfer, use appropriate plastic clamp or metal ferrule to seal off additive port tube.
8. Remove transfer set.
9. Mix contents of container thoroughly. Inspect final solution for discoloration and particulate matter. Check for leaks.

Two Port Container

1. Prior to adding lipid emulsion, mix amino acid and dextrose injection as shown in Figures 1-3.
2. Prepare lipid emulsion transfer set following instructions provided.
3. Attach transfer set to lipid emulsion container using aseptic technique.
4. Prepare medication port.
5. Using a 19 to 22 gauge needle, puncture resealable medication port.
6. Open clamp on transfer set and transfer lipid emulsion.
7. Remove needle.
8. Mix contents of container thoroughly. Inspect final solution for discoloration and particulate matter. Check for leaks.

Storage Once Lipids are Added:

Use promptly after mixing. Any storage with additives should be under refrigeration and limited to a brief period of time, no longer than 24 hours. After removal from refrigeration, use promptly and complete the infusion within 24 hours. Any mixture remaining must be discarded.

2.5 Dosing Considerations

- The dosage of CLINIMIX should be individualized based on the patient’s clinical condition (ability to adequately metabolize amino acids and dextrose), body weight and nutritional/fluid requirements, as well as additional energy given orally/enterally to the patient. Prior to initiating CLINIMIX the following patient information should be reviewed: all concomitant medications, gastrointestinal function and laboratory data such as electrolytes (including magnesium, calcium, and phosphorus), glucose, urea/creatinine, liver panel, complete blood count and triglyceride level (if adding lipid emulsion). Refer to the complete prescribing information of lipid emulsion for dosing information.
- CLINIMIX formulations have varying concentrations of protein and carbohydrate; thus infusion rates to achieve requirements will vary. Protein, caloric, fluid and electrolyte requirements all need to be taken into consideration when determining individual patient dosage needs.
- The dosage selection is based only on the recommended protein requirements. The maximum dextrose infusion rates and calorie and fluid requirements must also be considered when determining the clinically appropriate infusion rate for patients.
- CLINIMIX meets the total nutritional requirements for protein and dextrose in stable patients, and can be individualized to meet specific needs with the addition of nutrients.
- Total daily fluid requirements can be met beyond the volume of amino acids solution by supplementing with non-carbohydrate or carbohydrate-containing electrolyte solutions. In many patients, provision of adequate calories in the form of hypertonic dextrose may require the administration of exogenous insulin to prevent hyperglycemia and glycosuria.
- Prior to administration of CLINIMIX correct severe fluid, electrolyte and acid-base disorders.
- Monitor levels of serum potassium during therapy. It may be necessary to add potassium to the CLINIMIX admixture.
- Lipid emulsion administration should be considered with prolonged use (more than 5 days) of CLINIMIX in order to prevent essential fatty acid deficiency (EFAD). Serum lipids should be monitored for evidence of EFAD in patients maintained on fat-free parenteral nutrition. See prescribing information of lipid emulsion.
- The flow rate should be increased gradually. The flow rate must be adjusted taking into account the dose being administered, the daily volume intake, and the duration of the infusion.

2.6 Recommended Dosage in Adults

The recommended daily nutritional requirements for protein and dextrose compared to the amount of nutrition provided by CLINIMIX are shown in Table 1.

As indicated on an individual basis, maintenance vitamins, electrolytes, trace elements and other components (including lipids) should be administered as required to prevent deficiencies and complications from developing.

The maximum infusion rates in adult patients are show in Table 2.

In addition to meeting protein needs, the administration rate should be governed, especially during the first few day of therapy, by the patient’s tolerance to dextrose. Daily intake of amino acids and dextrose should be increased gradually to the maximum required dose as indicated by frequent determinations of blood glucose levels.

Table 1: Nutritional Comparison –Adult Patients
 | Recommended CLINIMIX Adult Dosage
 | CLINIMIX 4.25/5 | CLINIMIX 4.25/10 | CLINIMIX 5/15 | CLINIMIX 5/20 | CLINIMIX 6/5 | CLINIMIX 8/10 | CLINIMIX 8/14
Fluid (mL/kg/day) | 19 to 40 | 19 to 40 | 16 to 40 | 16 to 40 | 13 to 33 | 10 to 25 | 10 to 25
Protein [Protein is provided as amino acids. When infused intravenously amino acids are metabolized and utilized as the building blocks of protein.] (g/kg/day) (Nitrogen g/kg/day) | 0.8 to 1.7 (0.13 to 0.27) | 0.8 to 1.7 (0.13 to 0.27) | 0.8 to 2 (0.13 to 0.32) | 0.8 to 2 (0.13 to 0.32) | 0.8 to 2 (0.13 to 0.32) | 0.8 to 2 (0.13 to 0.32) | 0.8 to 2 (0.13 to 0.32)
Dextrose (g/kg/day) | 0.95 to 2 | 1.9 to 4 | 2.4 to 6 | 3.2 to 8 | 0.65 to 1.65 | 1 to 2.5 | 1.4 to 3.5

Table 2: Maximum Infusion Rate in Adult Patients
 |  | Maximum Infusion Rates in Adults Patients
 |  | CLINIMIX 4.25/5 | CLINIMIX 4.25/10 | CLINIMIX 5/15 | CLINIMIX 5/20 | CLINIMIX 6/5 | CLINIMIX 8/10 | CLINIMIX 8/14
Maximum Infusion Rate (mL/kg/hour) |  | 2.4 | 2.4 | 1.67 | 1.25 | 1.67 | 1.3 | 1.3
Corresponding infusion rate | Amino Acid (g/kg/hour) | 0.1 [Rate limiting factor] | 0.1 | 0.08 | 0.06 | 0.1 | 0.1 | 0.1
Corresponding infusion rate | Dextrose (g/kg/hour) | 0.12 | 0.24 | 0.25 | 0.25 | 0.08 | 0.13 | 0.18

2.7 Dosage Modifications in Patients with Kidney Disease

Prior to administration, correct severe fluid or electrolyte imbalances. Closely monitor serum electrolyte levels and adjust the volume of CLINIMIX administered as required [see Warnings and Precautions (5.10)].

Chronic kidney disease patients with less than nephrotic range proteinuria require 0.8 g of protein/kg/day. Chronic kidney disease patients with nephrotic range proteinuria require 0.8g of protein/kg/day plus 1g of protein for each gram of proteinuria. Patients needing dialysis should receive from 1.2 of protein/kg/day up to a maximum of 2.5 g of protein/kg/day depending on the nutritional status and the dialysis modality. Serum electrolyte levels should be closely monitored. The CLINIMIX dosage can be adjusted based on the severity of kidney disease, supplementing protein as indicated. If required, additional amino acids may be added to the CLINIMIX container or infused separately. Compatibility of additions should be evaluated by a pharmacist and questions may be directed to Baxter.

2.8 Recommended Dosage in Pediatric Patients

The dosage and constant infusion rate of intravenous dextrose must be selected with caution in pediatric patients, particularly neonates and low weight infants, because of the increased risk of hyperglycemia/hypoglycemia [see Use in Specific Populations (8.4)]. Frequent monitoring of serum glucose concentrations is required when dextrose is prescribed to pediatric patients, particularly neonates and low birth weight infants. The infusion rate and volume should be determined by the consulting physician experienced in pediatric intravenous fluid therapy.

In pediatric patients, CLINIMIX is dosed on the basis of protein provided as amino acids. The recommended dosage, by age group is provided in Tables 3 - 6. Infusion rates are based on protein and do not take carbohydrates, fluid or electrolytes into consideration.

This product does not contain the amino acids cysteine and taurine, considered conditionally essential for neonates and infants. If possible, these amino acids should be added to this product if used in this pediatric population.

Table 3: Preterm and Term Infants Less than 1 Month of Age
 | Recommended CLINIMIX Dosage in Preterm and Term Infants Less than 1 Month of Age
 | CLINIMIX 4.25/5 | CLINIMIX 4.25/10 | CLINIMIX 5/15 | CLINIMIX 5/20 | CLINIMIX 6/5 | CLINIMIX 8/10 | CLINIMIX 8/14
Infusion Rate Range (mL/kg/hr) | 2.9 to 3.9 | 2.9 to 3.9 | 2.5 to 3.3 | 2.5 to 3.3 | 2.1 to 2.8 | 1.6 to 2.1 | 1.6 to 2.1
Fluid (mL/kg/day) | 70 to 94 | 70 to 94 | 60 to 79 | 60 to 79 | 50 to 67 | 38.4 to 50 | 38.4 to 50
Protein [Protein is provided as amino acids. When infused intravenously amino acids are metabolized and utilized as the building blocks of protein.] (g/kg/day) (Nitrogen g/kg/day) | 3 to 4 (0.48 to 0.64) | 3 to 4 (0.48 to 0.64) | 3 to 4 (0.48 to 0.64) | 3 to 4 (0.48 to 0.64) | 3 to 4 (0.48 to 0.64) | 3 to 4 (0.48 to 0.64) | 3 to 4 (0.48 to 0.64)
Dextrose (g/kg/day) | 3.5 to 4.7 | 7 to 9.4 | 9 to 11.9 | 12 to 15.8 | 2.5 to 3.4 | 3.8 to 5 | 5.4 to 7

Table 4: Pediatric Patients 1 Month to Less than 1 Year of Age
 | Recommended CLINIMIX Dosage in Pediatric Patients 1 Month to Less than 1 Year of Age
 | CLINIMIX 4.25/5 | CLINIMIX 4.25/10 | CLINIMIX 5/15 | CLINIMIX 5/20 | CLINIMIX 6/5 | CLINIMIX 8/10 | CLINIMIX 8/14
Infusion Rate Range (mL/kg/hr) | 2 to 2.9 | 2 to 2.9 | 1.7 to 2.5 | 1.7 to 2.5 | 1.4 to 2.1 | 1 to 1.6 | 1 to 1.6
Fluid (mL/kg/day) | 48 to 70 | 48 to 70 | 41 to 60 | 41 to 60 | 33.6 to 50 | 24 to 38.4 | 24 to 38.4
Protein [Protein is provided as amino acids. When infused intravenously amino acids are metabolized and utilized as the building blocks of protein.] (g/kg/day) (Nitrogen g/kg/day) | 2 to 3 (0.32 to 0.48) | 2 to 3 (0.32 to 0.48) | 2 to 3 (0.32 to 0.48) | 2 to 3 (0.32 to 0.48) | 2 to 3 (0.32 to 0.48) | 2 to 3 (0.32 to 0.48) | 2 to 3 (0.32 to 0.48)
Dextrose (g/kg/day) | 2.4 to 3.5 | 4.8 to 7 | 6.1 to 9 | 8.2 to 12 | 1.7 to 2.5 | 2.4 to 3.8 | 3.4 to 5.4

Table 5: Pediatric Patients 1 Year to Less than 11 Years of Age
 | Recommended CLINIMIX Dosage in Pediatric Patients 1 Year to Less than 11 Years of Age
 | CLINIMIX 4.25/5 | CLINIMIX 4.25/10 | CLINIMIX 5/15 | CLINIMIX 5/20 | CLINIMIX 6/5 | CLINIMIX 8/10 | CLINIMIX 8/14
Infusion Rate Range (mL/kg/hr) | 1 to 2 | 1 to 2 | 0.8 to 1.7 | 0.8 to 1.7 | 0.7 to 1.4 | 0.5 to 1 | 0.5 to 1
Fluid (mL/kg/day) | 24 to 48 | 24 to 48 | 19 to 41 | 19 to 41 | 16.8 to 33.6 | 12 to 24 | 12 to 24
Protein [Protein is provided as amino acids. When infused intravenously amino acids are metabolized and utilized as the building blocks of protein.] (g/kg/day) (Nitrogen g/kg/day) | 1 to 2 (0.16 to 0.32) | 1 to 2 (0.16 to 0.32) | 1 to 2 (0.16 to 0.32) | 1 to 2 (0.16 to 0.32) | 1 to 2 (0.16 to 0.32) | 1 to 2 (0.16 to 0.32) | 1 to 2 (0.16 to 0.32)
Dextrose (g/kg/day) | 1.2 to 2.4 | 2.4 to 4.8 | 2.9 to 6.1 | 3.8 to 8.2 | 0.8 to 1.7 | 1.2 to 2.4 | 1.7 to 3.4

Table 6: Pediatric Patients 11 Years to 17 Years of Age
 | Recommended CLINIMIX Dosage in Pediatric Patients 11 Years to 17 Years of Age
 | CLINIMIX 4.25/5 | CLINIMIX 4.25/10 | CLINIMIX 5/15 | CLINIMIX 5/20 | CLINIMIX 6/5 | CLINIMIX 8/10 | CLINIMIX 8/14
Infusion Rate Range (mL/kg/hr) | 0.8 to 1.5 | 0.8 to 1.5 | 0.7 to 1.3 | 0.7 to 1.3 | 0.6 to 1 | 0.4 to 0.8 | 0.4 to 0.8
Fluid (mL/kg/day) | 19 to 36 | 19 to 36 | 17 to 31 | 17 to 31 | 14.4 to 24 | 9.6 to 19.2 | 9.6 to 19.2
Protein [Protein is provided as amino acids. When infused intravenously amino acids are metabolized and utilized as the building blocks of protein.] (g/kg/day) (Nitrogen g/kg/day) | 0.8 to 1.5 (0.13 to 0.24) | 0.8 to 1.5 (0.13 to 0.24) | 0.8 to 1.5 (0.13 to 0.24) | 0.8 to 1.5 (0.13 to 0.24) | 0.8 to 1.5 (0.13 to 0.24) | 0.8 to 1.5 (0.13 to 0.24) | 0.8 to 1.5 (0.13 to 0.24)
Dextrose (g/kg/day) | 1 to 1.8 | 1.9 to 3.6 | 2.5 to 4.7 | 3.4 to 6.2 | 0.7 to 1.2 | 1 to 1.9 | 1.4 to.2.7

2.9 Discontinuation of CLINIMIX

To reduce the risk of hypoglycemia after discontinuation, a gradual decrease in flow rate in the last hour of infusion should be considered.

3 DOSAGE FORMS AND STRENGTHS

CLINIMIX injection is available in 1000 mL and 2000 mL dual chamber containers. The individual chambers contain essential and nonessential amino acids and dextrose. Table 7 describes the individual components of CLINIMIX.

Table 7: INGREDIENTS PER 100mL OF CLINIMIX
Strength of CLINIMIX |  | CLINIMIX 4.25/5 sulfite‑free (4.25% Amino Acid in 5% Dextrose) Injection | CLINIMIX4.25/10 sulfite‑free (4.25% Amino Acid in 10% Dextrose) Injection | CLINIMIX 5/15 sulfite‑free (5% Amino Acid in 15% Dextrose) Injection | CLINIMIX 5/20 sulfite‑free (5% Amino Acid in 20% Dextrose) Injection | CLINIMIX 6/5 sulfite‑free (6% Amino Acid in 5% Dextrose) Injection | CLINIMIX 8/10 sulfite‑free (8% Amino Acid in 10% Dextrose) Injection | CLINIMIX 8/14 sulfite‑free (8% Amino Acid in 14% Dextrose) Injection
 | Dextrose Hydrous, USP (g/100 mL) | 5 | 10 | 15 | 20 | 5 | 10 | 14
 | Amino Acids (g/100 mL) | 4.25 | 4.25 | 5 | 5 | 6 | 8 | 8
 | Total Nitrogen (mg/100 mL) | 702 | 702 | 826 | 826 | 990 | 1320 | 1320
Essential Amino Acids (mg/100 mL) | Leucine | 311 | 311 | 365 | 365 | 438 | 584 | 584
Essential Amino Acids (mg/100 mL) | Isoleucine | 255 | 255 | 300 | 300 | 360 | 480 | 480
Essential Amino Acids (mg/100 mL) | Valine | 247 | 247 | 290 | 290 | 348 | 464 | 464
Essential Amino Acids (mg/100 mL) | Lysine (added as the hydrochloride salt) | 247 | 247 | 290 | 290 | 348 | 464 | 464
Essential Amino Acids (mg/100 mL) | Phenylalanine | 238 | 238 | 280 | 280 | 336 | 448 | 448
Essential Amino Acids (mg/100 mL) | Histidine | 204 | 204 | 240 | 240 | 288 | 384 | 384
Essential Amino Acids (mg/100 mL) | Threonine | 179 | 179 | 210 | 210 | 252 | 336 | 336
Essential Amino Acids (mg/100 mL) | Methionine | 170 | 170 | 200 | 200 | 240 | 320 | 320
Essential Amino Acids (mg/100 mL) | Tryptophan | 77 | 77 | 90 | 90 | 108 | 144 | 144
Nonessential Amino Acids (mg/100 mL) | Alanine | 880 | 880 | 1035 | 1035 | 1242 | 1656 | 1656
Nonessential Amino Acids (mg/100 mL) | Arginine | 489 | 489 | 575 | 575 | 690 | 920 | 920
Nonessential Amino Acids (mg/100 mL) | Glycine | 438 | 438 | 515 | 515 | 618 | 824 | 824
Nonessential Amino Acids (mg/100 mL) | Proline | 289 | 289 | 340 | 340 | 408 | 544 | 544
Nonessential Amino Acids (mg/100 mL) | Serine | 213 | 213 | 250 | 250 | 300 | 400 | 400
Nonessential Amino Acids (mg/100 mL) | Tyrosine | 17 | 17 | 20 | 20 | 24 | 32 | 32
Anion Profile (mEq/L) [Balanced by ions from amino acids.] | Acetate [Derived from glacial acetic acid (for pH adjustment).] | 37 | 37 | 42 | 42 | 53 | 71 | 71
Anion Profile (mEq/L) [Balanced by ions from amino acids.] | Chloride [Contributed by lysine hydrochloride and hydrochloric acid (for pH adjustment).] | 17 | 17 | 20 | 20 | 24 | 32 | 32
 | pH [pH of sulfite-free amino acid injection in the outlet port chamber may be adjusted with glacial acetic acid and pH of dextrose injection port chamber may be adjusted with hydrochloric acid.] (Range) | 6.0 (4.5 to 7.0) | 6.0 (4.5 to 7.0) | 6.0 (4.5 to 7.0) | 6.0 (4.5 to 7.0) | 6.0 (4.5 to 7.0) | 6.0 (4.5 to 7.0) | 6.0 (4.5 to 7.0)
 | Osmolarity (mOsmol/L) (calc) | 675 | 930 | 1255 | 1505 | 850 | 1308 | 1520
Caloric Content (kcal/L) | From Dextrose | 170 | 340 | 510 | 680 | 170 | 343 | 477
Caloric Content (kcal/L) | From Amino Acids | 170 | 170 | 200 | 200 | 240 | 320 | 320
Caloric Content (kcal/L) | TOTAL (Dextrose and Amino Acids) | 340 | 510 | 710 | 880 | 410 | 663 | 797

4 CONTRAINDICATIONS

The use of CLINIMIX is contraindicated in:

- Patients with known hypersensitivity to one or more amino acids or dextrose [see Warnings and Precautions (5.2)].
- Patients with inborn errors of amino acid metabolism due to risk of severe metabolic and neurologic complications.
- Patients with pulmonary edema or acidosis due to low cardiac output.

5 WARNINGS AND PRECAUTIONS

5.1 Pulmonary Embolism due to Pulmonary Vascular Precipitates

Pulmonary vascular precipitates causing pulmonary vascular emboli and pulmonary distress have been reported in patients receiving parenteral nutrition. In some cases, fatal outcomes due to pulmonary embolism have occurred. CLINIMIX contains no added phosphorus. Patients, especially those with hypophosphatemia, may require the addition of phosphate. To prevent hypocalcemia, calcium supplementation should always accompany phosphate administration. Excessive addition of calcium and phosphate increases the risk of the formation of calcium phosphate precipitates. Precipitates have been reported even in the absence of phosphate salt in the solution. Precipitation following passage through an in-line filter and suspected in vivo precipitate formation has also been reported. If signs of pulmonary distress occur, stop the infusion and initiate a medical evaluation. In addition to inspection of the solution [see Dosage and Administration (2.1, 2.2, 2.3, 2.4)], the infusion set and catheter should also periodically be checked for precipitates.

5.2 Hypersensitivity Reactions

Hypersensitivity/infusion reactions including anaphylaxis have been reported with CLINIMIX. Stop infusion immediately and treat patient accordingly if any signs or symptoms of a hypersensitivity reaction develop. Signs or symptoms may include: hypotension, hypertension, peripheral cyanosis, tachycardia, dyspnea, vomiting, nausea, urticaria, rash, pruritus, erythema, hyperhidrosis, pyrexia, and chills.

5.3 Risk of Infections

Patients who require parenteral nutrition are at high risk of infections because the nutritional components of these solutions can support microbial growth. Infection and sepsis may also occur as a result of the use of intravenous catheters to administer parenteral nutrition.

The risk of infection is increased in patients with malnutrition-associated immunosuppression, hyperglycemia exacerbated by dextrose infusion, long-term use and poor maintenance of intravenous catheters, or immunosuppressive effects of other concomitant conditions, drugs, or other components of the parenteral formulation (e.g., lipid emulsion).

To decrease the risk of infection, ensure aseptic technique in catheter placement and maintenance, as well as aseptic technique in the preparation and administration of the nutritional formula.

Monitor for signs and symptoms (including fever and chills) of early infections, including laboratory test results (including leukocytosis and hyperglycemia) and frequent checks of the parenteral access device and insertion site for edema, redness and discharge.

5.4 Refeeding Syndrome

Refeeding severely undernourished patients may result in refeeding syndrome, characterized by the intracellular shift of potassium, phosphorus, and magnesium as the patient becomes anabolic. Thiamine deficiency and fluid retention may also develop. To prevent these complications, monitor severely undernourished patients and slowly increase nutrient intakes.

5.5 Hyperglycemia or Hyperosmolar Hyperglycemic State

When using CLINIMIX in patients with diabetes mellitus, impaired glucose tolerance may worsen hyperglycemia. Administration of dextrose at a rate exceeding the patient’s utilization rate may lead to hyperglycemia, coma, and death. Patients with dehydration, resulting in a transient reduction in glomerular filtration rate and pre-renal azotemia, may be a greater risk of developing hyperosmolar hyperglycemic state. Monitor blood glucose levels and treat hyperglycemia to maintain optimum levels while administering CLINIMIX. Insulin may be administered or adjusted to maintain optimal blood glucose levels during CLINIMIX administration.

5.6 Vein Damage and Thrombosis

Solutions with osmolarity of 900 mOsm/L or greater must be infused through a central catheter. CLINIMIX solutions containing more than 5% dextrose have an osmolarity greater than or equal to 900 mOsm/L. CLINIMIX 4.25/10, 5/15, 5/20, 8/10 and 8/14 are indicated for administration into a central vein only, such as the superior vena cava [see Dosage and Administration (2.2)]. The infusion of hypertonic nutrient injections into a peripheral vein may result in vein irritation, vein damage, and/or thrombosis.

CLINIMIX 4.25/5 and 6/5 are indicated for peripheral administration, or may be infused into a central vein [see Dosage and Administration (2.2)]. The primary complication of peripheral access is venous thrombophlebitis, which manifests as pain, erythema, tenderness or a palpable cord. Remove the catheter as soon as possible, if thrombophlebitis develops.

5.7 Hepatobiliary Disorders

Hepatobiliary disorders are known to develop in some patients without preexisting liver disease who receive parenteral nutrition, including cholecystitis, cholelithiasis, cholestasis, hepatic steatosis, fibrosis and cirrhosis, possibly leading to hepatic failure. The etiology of these disorders is thought to be multifactorial and may differ between patients.

Increase in blood ammonia levels and hyperammonemia may occur in patients receiving amino acid solutions. In some patients this may indicate hepatic insufficiency or the presence of an inborn error of amino acid metabolism [see Contraindications (4)].

Monitor liver function parameters and ammonia levels. Patients developing signs of hepatobiliary disorders should be assessed early by a clinician knowledgeable in liver diseases in order to identify possible causative and contributory factors, and possible therapeutic and prophylactic interventions.

5.8 Aluminum Toxicity

CLINIMIX contains no more than 25 mcg/L of aluminum. The aluminum contained in CLINIMIX may reach toxic levels with prolonged administration in patients with impaired kidney function. Preterm infants are at a greater risk because their kidneys are immature, and they require large amounts of calcium and phosphate solutions, which contain aluminum. Patients with impaired kidney function, including preterm infants, who receive parenteral levels of aluminum at greater than 4 to 5 mcg/kg/day, accumulate aluminum at levels associated with central nervous system and bone toxicity. Tissue loading may occur at even lower rates of administration.

5.9 Risk of Parenteral Nutrition Associated Liver Disease

Parenteral Nutrition Associated Liver Disease (PNALD) has been reported in patients who receive parenteral nutrition for extended periods of time, especially preterm infants, and can present as cholestasis or steatohepatitis. The exact etiology is unknown and is likely multifactorial. If CLINIMIX treated patients develop liver test abnormalities consider discontinuation or dosage reduction.

5.10 Electrolyte Imbalance and Fluid Overload

Patients with abnormal renal function due to pre-renal azotemia, renal obstruction, or intrinsic kidney disease may be at increased risk of electrolyte and fluid volume imbalance. Patients with cardiac insufficiency due to left ventricular systolic dysfunction are susceptible to excess fluid accumulation. Use CLINIMIX with caution in patients with cardiac insufficiency or kidney disease. CLINIMIX dosage may require adjustment with specific attention to fluid, protein, and electrolyte content in these patients.

Monitor renal function parameters. Patients developing signs of kidney disease should be assessed early by a clinician knowledgeable in kidney disease in order to determine the appropriate CLINIMIX dosage and other treatment options.

5.11 Monitoring/Laboratory Tests

Monitor fluid and electrolyte status, serum osmolarity, blood glucose, liver and kidney function, blood count and coagulation parameters throughout treatment.

Patients receiving CLINIMIX should be monitored frequently and their electrolyte requirements individualized.

6 ADVERSE REACTIONS

The following serious adverse reactions are discussed in greater detail in other sections of the prescribing information.

- Pulmonary embolism due to pulmonary vascular precipitates [see Warnings and Precautions (5.1)]
- Hypersensitivity reactions [see Warnings and Precautions (5.2)]
- Risk of Infections [see Warnings and Precautions (5.3)]
- Refeeding syndrome [see Warnings and Precautions (5.4)]
- Hyperglycemia or hyperosmolar hyperglycemic state [see Warnings and Precautions (5.5)]
- Vein damage and thrombosis [see Warnings and Precautions (5.6)]
- Hepatobiliary disorders [see Warnings and Precautions (5.7)]
- Parenteral Nutrition Associated Liver Disease [see Warnings and Precautions (5.9)]
- Electrolyte imbalance and fluid overload [see Warnings and Precautions (5.10)]

The following adverse reactions from voluntary reports or clinical studies have been reported with CLINIMIX. Because many of these reactions were reported voluntarily from a population of uncertain size, it is not always possible to reliably estimate their frequency or establish a causal relationship to drug exposure.

- Diuresis
- Extravasation
- Glycosuria
- Hyperglycemia
- Hyperosmolar coma

8 USE IN SPECIFIC POPULATIONS

8.1 Pregnancy

Risk Summary

There are no adequate or well-controlled studies in pregnant women with CLINIMIX. Additionally, animal reproduction studies have not been conducted with amino acids and electrolytes and dextrose. It is not known whether CLINIMIX can cause fetal harm when administered to a pregnant woman.

The estimated background risk of major birth defects and miscarriage for the indicated population is unknown. However, the estimated background risk in the U.S. general population of major birth defects is 2 to 4% and of miscarriage is 15 to 20% of clinically recognized pregnancies.

Clinical Considerations

Disease-Associated Maternal and/or Embryo-Fetal Risk

Based on clinical practice guidelines, parenteral nutrition should be considered in cases of severe maternal malnutrition where nutritional requirements cannot be fulfilled by the enteral route because of the risks to the fetus associated with severe malnutrition, such as preterm delivery, low birth weight, intrauterine growth restriction, congenital malformations and perinatal mortality.

8.2 Lactation

Risk Summary

It is not known whether CLINIMIX is present in human milk. There are no data on the effects of CLINIMIX on the breastfed infant or on milk production. The developmental and health benefits of breastfeeding should be considered along with the mother’s clinical need for CLINIMIX and any potential adverse effects on the breastfed child from CLINIMIX or from the underlying maternal condition.

8.4 Pediatric Use

Safety and effectiveness of CLINIMIX in pediatric patients have not been established by adequate and well-controlled studies. Use of dextrose, amino acid infusions and electrolytes in pediatric patients is based on clinical practice [see Dosage and Administration (2.8)].

Newborns, especially those born premature and with low birth weight, are at increased risk of developing hypo – or hyperglycemia and therefore need close monitoring during treatment with intravenous glucose solutions to ensure adequate glycemic control in order to avoid potential long term adverse effects. Hypoglycemia in the newborn can cause prolonged seizures, coma and brain damage. Hyperglycemia has been associated with intraventricular hemorrhage, late onset bacterial and fungal infection, retinopathy of prematurity, necrotizing enterocolitis, bronchopulmonary dysplasia, prolonged length of hospital stay, and death. Plasma electrolyte concentrations should be closely monitored in the pediatric population as this population may have impaired ability to regulate fluids and electrolytes.

Because of immature renal function, preterm infants receiving prolonged treatment with CLINIMIX may be at risk of aluminum toxicity [see Warnings and Precautions (5.8)].

Patients, including pediatric patients, may be at risk for Parenteral Nutrition Associated Liver Disease (PNALD) [see Warnings and Precautions (5.9)].

Hyperammonemia is of special significance in infants (birth to two years). This reaction appears to be related to a deficiency of the urea cycle amino acids of genetic or product origin. It is essential that blood ammonia be measured frequently in infants [see Warnings and Precautions (5.7)].

8.5 Geriatric Use

Clinical studies of CLINIMIX did not include sufficient numbers of subjects aged 65 and over to determine whether they respond differently from other younger subjects. Other reported clinical experience has not identified differences in responses between the elderly and younger patients.

In general, dose selection for an elderly patient should be cautious, usually starting at the low end of the dosing range, reflecting the greater frequency of decreased hepatic, renal, or cardiac function, and of concomitant disease or drug therapy.

10 OVERDOSAGE

An increased infusion rate of CLINIMIX cause hyperglycemia, hyperosmolality, and adverse effects on water and electrolyte balance [see Warnings and Precautions (5.5, 5.10)].

Severe hyperglycemia and severe dilutional hyponatremia, and their complications, can be fatal.

Discontinue infusion and institute appropriate corrective measures in the event of overhydration or solute overload during therapy, with particular attention to respiratory and cardiovascular systems.

For current information on the management of poisoning or overdosage, contact the National Poison Control Center at 1-800-222-1222 or www.poison.org.

11 DESCRIPTION

CLINIMIX sulfite-free (amino acids in dextrose) injection for intravenous use consists of sterile, nonpyrogenic, hypertonic solutions in a dual chamber container.

The outlet port chamber contains essential and nonessential amino acids. The formulas for the individual amino acids found in CLINIMIX sulfite-free (amino acids in dextrose) injections are provided in Table 8.

Table 8: Formulas for Amino Acids
Essential Amino Acids
Leucine | (CH3)2 CHCH2CH (NH2) COOH
Isoleucine | CH3CH2CH (CH3) CH (NH2) COOH
Valine | (CH3)2 CHCH (NH2) COOH
Lysine (added as the hydrochloride salt) | H2N (CH2)4 CH (NH2) COOH
Phenylalanine | (C6H5) CH2 CH (NH2) COOH
Histidine | (C3H3N2) CH2CH (NH2) COOH
Threonine | CH3CH (OH) CH (NH2) COO
Methionine | CH3S (CH2)2 CH (NH2) COOH
Tryptophan | (C8H6N) CH2 CH (NH2) COOH
Nonessential Amino Acids
Alanine | CH3CH (NH2) COOH
Arginine | H2NC (NH) NH (CH2)3 CH (NH2) COOH
Glycine | H2NCH2COOH
Proline | [(CH2)3 NH CH] COOH
Serine | HOCH2CH (NH2) COOH
Tyrosine | [C6H4 (OH)] CH2CH (NH2) COOH

The injection port chamber contains dextrose. Dextrose, USP, is chemically designated D-glucose, monohydrate (C6H12O6 • H2O) and has the following structure:

Dextrose is derived from corn.

See Table 7 for composition, pH, osmolarity, ionic concentration and caloric content of the admixed product [see Dosage Forms and Strengths (3)].

The dual chamber container is a lipid-compatible plastic container (PL 2401 Plastic).

CLINIMIX contains no more than 25 mcg/L of aluminum.

12 CLINICAL PHARMACOLOGY

12.1 Mechanism of Action

CLINIMIX is used as a supplement of nutrition in patients, providing macronutrients (amino acids and dextrose) parenterally.

The amino acids provide the structural units that make up proteins and are used to synthesize proteins and other biomolecules or are oxidized to urea and carbon dioxide as a source of energy.

The administered dextrose is oxidized to carbon dioxide and water, yielding energy.

12.3 Pharmacokinetics

The disposition of infused amino acids and dextrose, are essentially the same as those absorbed from ordinary food.

16 HOW SUPPLIED/STORAGE AND HANDLING

CLINIMIX (amino acids in dextrose) injection (sulfite-free) is available in 1000 mL and 2000 mL volumes (See Table 9).

Table 9: CLINIMIX Formulations (per 07-19-00-3604 and BE-30-03-648)
After mixing, the product represents | 1000 mL Code and NDC Number | 2000 mL Code and NDC Number
CLINIMIX 4.25/5 sulfite‑free (4.25% Amino Acid in 5% Dextrose) Injection | Code 2B7726 NDC 0338‑1133‑03 | Code 2B7704 NDC 0338‑1089‑04
CLINIMIX 4.25/10 sulfite‑free (4.25% Amino Acid in 10% Dextrose) Injection | Code 2B7727 NDC 0338‑1134‑03 | Code 2B7705 NDC 0338‑1091‑04
CLINIMIX 5/15 sulfite‑free (5% Amino Acid in 15% Dextrose) Injection | Code 2B7730 NDC 0338‑1137‑03 | Code 2B7709 NDC 0338‑1099‑04
CLINIMIX 5/20 sulfite‑free (5% Amino Acid in 20% Dextrose) Injection | Code 2B7731 NDC 0338‑1138‑03 | Code 2B7710 NDC 0338‑1101‑04
CLINIMIX 6/5 sulfite‑free (6% Amino Acid in 5% Dextrose) Injection | Code EADB9913 NDC 0338‑0198-06 | _____
CLINIMIX 8/10 sulfite‑free (8% Amino Acid in 10% Dextrose) Injection | Code EADB9933 NDC 0338‑0188-06 | Code EADB9935 NDC 0338‑0194-04
CLINIMIX 8/14 sulfite‑free (8% Amino Acid in 14% Dextrose) Injection | Code EADB9953 NDC 0338‑0180-06 | Code EADB9955 NDC 0338‑0184-04

Table 9: CLINIMIX Formulations (per BE-30-04-047)

After mixing, the product represents | 1000 mL Code and NDC Number | 2000 mL Code and NDC Number
CLINIMIX 4.25/5 sulfite‑free (4.25% Amino Acid in 5% Dextrose) Injection | Code 2B7726L NDC 0338‑7001-01 | Code 2B7704L NDC 0338‑7003-01
CLINIMIX 4.25/10 sulfite‑free (4.25% Amino Acid in 10% Dextrose) Injection | Code 2B7727L NDC 0338‑7005-01 | Code 2B7705L NDC 0338‑7007-01
CLINIMIX 5/15 sulfite‑free (5% Amino Acid in 15% Dextrose) Injection | Code 2B7730L NDC 0338‑7009-01 | Code 2B7709L NDC 0338‑7011-01
CLINIMIX 5/20 sulfite‑free (5% Amino Acid in 20% Dextrose) Injection | Code 2B7731L NDC 0338‑7013-01 | Code 2B7710L NDC 0338‑7015-01
CLINIMIX 6/5 sulfite‑free (6% Amino Acid in 5% Dextrose) Injection | Code EADB9913 NDC 0338‑0198-06 | _____
CLINIMIX 8/10 sulfite‑free (8% Amino Acid in 10% Dextrose) Injection | Code EADB9933 NDC 0338‑0188-06 | Code EADB9935 NDC 0338‑0194-04
CLINIMIX 8/14 sulfite‑free (8% Amino Acid in 14% Dextrose) Injection | Code EADB9953 NDC 0338‑0180-06 | Code EADB9955 NDC 0338‑0184-04

Minimize exposure of CLINIMIX to heat and avoid excessive heat.

Protect from freezing.

Store CLINIMIX at room temperature (25°C/77°F) (may briefly store at up to 40°C/104°F).

Refrigerated storage is limited to 9 days once the protective overwrap has been opened.

Do not use if the protective overwrap has been previously opened or damaged.

For storage of admixed solutions see Dosage and Administration (2.3, 2.4).

17 PATIENT COUNSELING INFORMATION

Inform patients, caregivers, or home healthcare providers of the following risks of CLINIMIX:

- Pulmonary embolism due to pulmonary vascular precipitates [see Warnings and Precautions (5.1)]
- Hypersensitivity reactions [see Warnings and Precautions (5.2)]
- Risk of Infections [see Warnings and Precautions (5.3)]
- Refeeding syndrome [see Warnings and Precautions (5.4)]
- Hyperglycemia or hyperosmolar hyperglycemic state [see Warnings and Precautions (5.5)]
- Vein damage and thrombosis [see Warnings and Precautions (5.6)]
- Hepatobiliary disorders [see Warnings and Precautions (5.7)]
- Aluminum toxicity [see Warnings and Precautions (5.8)]
- Parenteral Nutrition Associated Liver Disease (PNALD) [see Warnings and Precautions (5.9)]
- Electrolyte imbalance and fluid overload [see Warnings and Precautions (5.10)]

Baxter Healthcare Corporation
  Deerfield, IL 60015 USA
Baxter and Clinimix are registered trademarks of Baxter International Inc.
07-19-00-360 [Applies to Baxter Healthcare Corporation, Jayuya – Puerto Rico manufacturing plant]
BE-30-03-648 [Applies to Baxter SA, Lessines – Belgium manufacturing plant for Clinimix 6/5, Clinimix 8/10 and Clinimix 8/14]
BE-30-04-047 [Applies to Baxter SA, Lessines – Belgium manufacturing plant for the other Clinimix formulations]

PACKAGE LABEL - PRINCIPAL DISPLAY PANEL

Container Label

LOT EXP
2B7727 NDC 0338-1134-03

CLINIMIX
4.25/10
SULFITE-FREE

(4.25% Amino Acids
in 10% Dextrose)
Injection

500 mL INJECTION PORT CHAMBER
20% Dextrose Injection USP

500 mL OUTLET PORT CHAMBER
8.5% Amino Acid Injection

Rx Only

ACTIVATE SEAL AND
MIX THOROUGHLY BEFORE USE

SEE PRESCRIBING INFORMATION FOR INSTRUCTIONS ON
ACTIVATION

AFTER MIXING THE PRODUCT REPRESENTS 1000 mL

REFRIGERATED STORAGE IS LIMITED TO 9 DAYS

A SLIGHT YELLOW COLOR DOES NOT ALTER THE QUALITY
AND EFFICACY OF THIS PRODUCT

ASK PHARMACIST ABOUT ADDITIVE COMPATIBILITY

CONTENTS OF EACH 100 mL OF THE ADMIXED
INJECTION
DEXTROSE HYDROUS USP 10 g

ESSENTIAL AMINO ACIDS
LEUCINE 311 mg
ISOLEUCINE 255 mg
VALINE 247 mg
LYSINE (ADDED AS THE
HYDROCHLORIDE SALT) 247 mg
PHENYLALANINE 238 mg
HISTIDINE 204 mg
THREONINE 179 mg
METHIONINE 170 mg
TRYPTOPHAN 77 mg

NONESSENTIAL AMINO ACIDS
ALANINE 880 mg
ARGININE 489 mg
GLYCINE 438 mg
PROLINE 289 mg
SERINE 213 mg
TYROSINE 17 mg

mEq/L
ACETATE 37
CHLORIDE 17

BALANCED BY IONS FROM AMINO ACIDS

pH ADJUSTED WITH GLACIAL ACETIC ACID

STERILE
SINGLE DOSE CONTAINER

ROOM TEMPERATURE (25°C/77°F)

AVOID EXCESSIVE HEAT

PROTECT FROM FREEZING

SEE PRESCRIBING INFORMATION

Baxter Logo
BAXTER HEALTHCARE CORPORATION
DEERFIELD IL 60015 USA
MADE IN USA

Container Label

LOT EXP

2B7726 NDC 0338-1133-03

CLINIMIX

4.25/5

SULFITE-FREE

(4.25% Amino Acids
in 5% Dextrose)
Injection

500 mL INJECTION PORT CHAMBER
10% Dextrose Injection USP

500 mL OUTLET PORT CHAMBER
8.5% Amino Acid Injection

ACTIVATE SEAL AND
MIX THOROUGHLY BEFORE USE

SEE PRESCRIBING INFORMATION FOR INSTRUCTIONS ON

ACTIVATION

AFTER MIXING THE PRODUCT REPRESENTS 1000 mL

REFRIGERATED STORAGE IS LIMITED TO 9 DAYS

A SLIGHT YELLOW COLOR DOES NOT ALTER THE QUALITY

AND EFFICACY OF THIS PRODUCT

ASK PHARMACIST ABOUT ADDITIVE COMPATIBILITY

CONTENTS OF EACH 100 mL OF THE ADMIXED
INJECTION
DEXTROSE HYDROUS USP 5 g

ESSENTIAL AMINO ACIDS
LEUCINE 311 mg
ISOLEUCINE 255 mg
VALINE 247 mg
LYSINE (ADDED AS THE
HYDROCHLORIDE SALT) 247 mg
PHENYLALANINE 238 mg
HISTIDINE 204 mg
THREONINE 179 mg
METHIONINE 170 mg
TRYPTOPHAN 77 mg

NONESSENTIAL AMINO ACIDS
ALANINE 880 mg
ARGININE 489 mg
GLYCINE 438 mg
PROLINE 289 mg
SERINE 213 mg
TYROSINE 17 mg

mEq/L
ACETATE 37
CHLORIDE 17

BALANCED BY IONS FROM AMINO ACIDS

pH ADJUSTED WITH GLACIAL ACETIC ACID

STERILE
SINGLE DOSE CONTAINER

ROOM TEMPERATURE (25°C/77°F)

AVOID EXCESSIVE HEAT

PROTECT FROM FREEZING

SEE PRESCRIBING INFORMATION

Baxter Logo

BAXTER HEALTHCARE CORPORATION
DEERFIELD IL 60015 USA
MADE IN USA

Container Label

LOT EXP

2B7704 NDC 0338-1089-04

CLINIMIX 4.25/5
SULFITE-FREE
(4.25% Amino Acid
in 5% Dextrose)
Injection

1000 mL INJECTION PORT CHAMBER
10% Dextrose Injection USP

1000 mL OUTLET PORT CHAMBER
8.5% Amino Acid Injection

Rx Only

ACTIVATE SEAL AND
MIX THOROUGHLY BEFORE USE

SEE PRESCRIBING INFORMATION FOR INSTRUCTIONS ON

ACTIVATION

AFTER MIXING THE PRODUCT REPRESENTS 2000 mL

REFRIGERATED STORAGE IS LIMITED TO 9 DAYS

A SLIGHT YELLOW COLOR DOES NOT ALTER THE QUALITY

AND EFFICACY OF THIS PRODUCT

ASK PHARMACIST ABOUT ADDITIVE COMPATIBILITY

CONTENTS OF EACH 100 mL OF THE
ADMIXED INJECTIONDEXTROSE HYDROUS USP 5 g

ESSENTIAL AMINO ACIDS
LEUCINE 311 mg
ISOLEUCINE 255 mg
VALINE 247 mg
LYSINE (ADDED AS THE
HYDROCHLORIDE SALT) 247 mg
PHENYLALANINE 238 mg
HISTIDINE 204 mg
THREONINE 179 mg
METHIONINE 170 mg
TRYPTOPHAN 77 mg

NONESSENTIAL AMINO ACIDS
ALANINE 880 mg
ARGININE 489 mg
GLYCINE 438 mg
PROLINE 289 mg
SERINE 213 mg
TYROSINE 17 mg

mEq/L
ACETATE 37
CHLORIDE 17

BALANCED BY IONS FROM AMINO ACIDS
pH ADJUSTED WITH GLACIAL ACETIC ACID

STERILE
SINGLE DOSE CONTAINER

ROOM TEMPERATURE (25°C/77°F)

AVOID EXCESSIVE HEAT

PROTECT FROM FREEZING

SEE PRESCRIBING INFORMATION

Baxter Logo
BAXTER HEALTHCARE CORPORATION
DEERFIELD IL 60015 USA
MADE IN USA

Container Label

LOT EXP

2B7705 NDC 0338-1091-04

CLINIMIX 4.25/10
SULFITE-FREE
(4.25% Amino Acid
in 10% Dextrose)
Injection

1000 mL INJECTION PORT CHAMBER
20% Dextrose Injection USP

1000 mL OUTLET PORT CHAMBER
8.5% Amino Acid Injection

Rx Only

ACTIVATE SEAL AND
MIX THOROUGHLY BEFORE USE

SEE PRESCRIBING INFORMATION FOR INSTRUCTIONS ON

ACTIVATION

AFTER MIXING THE PRODUCT REPRESENTS 2000 mL

REFRIGERATED STORAGE IS LIMITED TO 9 DAYS

A SLIGHT YELLOW COLOR DOES NOT ALTER THE QUALITY

AND EFFICACY OF THIS PRODUCT

ASK PHARMACIST ABOUT ADDITIVE COMPATIBILITY

CONTENTS OF EACH 100 mL OF THE
ADMIXED INJECTION

DEXTROSE HYDROUS USP 10 g

ESSENTIAL AMINO ACIDS
LEUCINE 311 mg
ISOLEUCINE 255 mg
VALINE 247 mg
LYSINE (ADDED AS THE
HYDROCHLORIDE SALT) 247 mg
PHENYLALANINE 238 mg
HISTIDINE 204 mg
THREONINE 179 mg
METHIONINE 170 mg
TRYPTOPHAN 77 mg

NONESSENTIAL AMINO ACIDS
ALANINE 880 mg
ARGININE 489 mg
GLYCINE 438 mg
PROLINE 289 mg
SERINE 213 mg
TYROSINE 17 mg

mEq/L
ACETATE 37
CHLORIDE 17

BALANCED BY IONS FROM AMINO ACIDS
pH ADJUSTED WITH GLACIAL ACETIC ACID

STERILE
SINGLE DOSE CONTAINER

ROOM TEMPERATURE (25°C/77°F)

AVOID EXCESSIVE HEAT

PROTECT FROM FREEZING

SEE PRESCRIBING INFORMATION

Baxter Logo
BAXTER HEALTHCARE CORPORATION
DEERFIELD IL 60015 USA
MADE IN USA

Container Label

LOT EXP

2B7730 NDC 0338-1137-03

CLINIMIX
5/15
SULFITE-FREE
(5% Amino Acid
in 15% Dextrose)
Injection

500 mL INJECTION PORT CHAMBER
30% Dextrose Injection USP

500 mL OUTLET PORT CHAMBER
10% Amino Acid Injection

Rx Only

ACTIVATE SEAL AND
MIX THOROUGHLY BEFORE USE

SEE PRESCRIBING INFORMATION FOR INSTRUCTIONS ON

ACTIVATION

AFTER MIXING THE PRODUCT REPRESENTS 1000 mL

REFRIGERATED STORAGE IS LIMITED TO 9 DAYS

A SLIGHT YELLOW COLOR DOES NOT ALTER THE QUALITY

AND EFFICACY OF THIS PRODUCT

ASK PHARMACIST ABOUT ADDITIVE COMPATIBILITY

CONTENTS OF EACH 100 mL OF THE
ADMIXED INJECTION

DEXTROSE HYDROUS USP 15 g

ESSENTIAL AMINO ACIDS
LEUCINE 365 mg
ISOLEUCINE 300 mg
VALINE 290 mg
LYSINE (ADDED AS THE
HYDROCHLORIDE SALT) 290 mg
PHENYLALANINE 280 mg
HISTIDINE 240 mg
THREONINE 210 mg
METHIONINE 200 mg
TRYPTOPHAN 90 mg

NONESSENTIAL AMINO ACIDS
ALANINE 1035 mg
ARGININE 575 mg
GLYCINE 515 mg
PROLINE 340 mg
SERINE 250 mg
TYROSINE 20 mg

mEq/L
ACETATE 42
CHLORIDE 20

BALANCED BY IONS FROM AMINO ACIDS
pH ADJUSTED WITH GLACIAL ACETIC ACID

STERILE
SINGLE DOSE CONTAINER

ROOM TEMPERATURE (25°C/77°F)

AVOID EXCESSIVE HEAT

PROTECT FROM FREEZING

SEE PRESCRIBING INFORMATION

Baxter Logo
BAXTER HEALTHCARE CORPORATION
DEERFIELD IL 60015 USA
MADE IN USA

Container Label

LOT EXP

2B7709 NDC 0338-1099-04

CLINIMIX
5/15
SULFITE-FREE
(5% Amino Acid
in 15% Dextrose)
Injection

1000 mL INJECTION PORT CHAMBER
30% Dextrose Injection USP

1000 mL OUTLET PORT CHAMBER
10% Amino Acid Injection

Rx Only

ACTIVATE SEAL AND
MIX THOROUGHLY BEFORE USE

SEE PRESCRIBING INFORMATION FOR INSTRUCTIONS ON

ACTIVATION

AFTER MIXING THE PRODUCT REPRESENTS 2000 mL

REFRIGERATED STORAGE IS LIMITED TO 9 DAYS

A SLIGHT YELLOW COLOR DOES NOT ALTER THE QUALITY

AND EFFICACY OF THIS PRODUCT

ASK PHARMACIST ABOUT ADDITIVE COMPATIBILITY

CONTENTS OF EACH 100 mL OF THE
ADMIXED INJECTION

DEXTROSE HYDROUS USP 15 g

ESSENTIAL AMINO ACIDS
LEUCINE 365 mg
ISOLEUCINE 300 mg
VALINE 290 mg
LYSINE (ADDED AS THE
HYDROCHLORIDE SALT) 290 mg
PHENYLALANINE 280 mg
HISTIDINE 240 mg
THREONINE 210 mg
METHIONINE 200 mg
TRYPTOPHAN 90 mg

NONESSENTIAL AMINO ACIDS
ALANINE 1035 mg
ARGININE 575 mg
GLYCINE 515 mg
PROLINE 340 mg
SERINE 250 mg
TYROSINE 20 mg

mEq/L
ACETATE 42
CHLORIDE 20

BALANCED BY IONS FROM AMINO ACIDS
pH ADJUSTED WITH GLACIAL ACETIC ACID

STERILE
SINGLE DOSE CONTAINER

ROOM TEMPERATURE (25°C/77°F)

AVOID EXCESSIVE HEAT

PROTECT FROM FREEZING

SEE PRESCRIBING INFORMATION

Baxter Logo
BAXTER HEALTHCARE CORPORATION
DEERFIELD IL 60015 USA
MADE IN USA

Container Label

LOT EXP

2B7731 NDC 0338-1138-03

CLINIMIX
5/
SULFITE-FREE
(5% Amino Acid
in 20% Dextrose)
Injection

500 mL INJECTION PORT CHAMBER
40% Dextrose Injection USP

500 mL OUTLET PORT CHAMBER
10% Amino Acid Injection

Rx Only

ACTIVATE SEAL AND
MIX THOROUGHLY BEFORE USE

SEE PRESCRIBING INFORMATION FOR INSTRUCTIONS ON

ACTIVATION

AFTER MIXING THE PRODUCT REPRESENTS 1000 mL

REFRIGERATED STORAGE IS LIMITED TO 9 DAYS

A SLIGHT YELLOW COLOR DOES NOT ALTER THE QUALITY

AND EFFICACY OF THIS PRODUCT

ASK PHARMACIST ABOUT ADDITIVE COMPATIBILITY

CONTENTS OF EACH 100 mL OF THE
ADMIXED INJECTION

DEXTROSE HYDROUS USP 20 g

ESSENTIAL AMINO ACIDS
LEUCINE 365 mg
ISOLEUCINE 300 mg
VALINE 290 mg
LYSINE (ADDED AS THE
HYDROCHLORIDE SALT) 290 mg
PHENYLALANINE 280 mg
HISTIDINE 240 mg
THREONINE 210 mg
METHIONINE 200 mg
TRYPTOPHAN 90 mg

NONESSENTIAL AMINO ACIDS
ALANINE 1035 mg
ARGININE 575 mg
GLYCINE 515 mg
PROLINE 340 mg
SERINE 250 mg
TYROSINE 20 mg

mEq/L
ACETATE 42
CHLORIDE 20

BALANCED BY IONS FROM AMINO ACIDS
pH ADJUSTED WITH GLACIAL ACETIC ACID

STERILE
SINGLE DOSE CONTAINER

ROOM TEMPERATURE (25°C/77°F)

AVOID EXCESSIVE HEAT

PROTECT FROM FREEZING

SEE PRESCRIBING INFORMATION

Baxter Logo
BAXTER HEALTHCARE CORPORATION
DEERFIELD IL 60015 USA
MADE IN USA

Container Label

LOT EXP

2B7710 NDC 0338-1101-04

CLINIMIX
5/20
SULFITE-FREE
(5% Amino Acid
in 20% Dextrose)
Injection

1000 mL INJECTION PORT CHAMBER
40% Dextrose Injection USP

1000 mL OUTLET PORT CHAMBER
10% Amino Acid Injection

Rx Only

ACTIVATE SEAL AND
MIX THOROUGHLY BEFORE USE

SEE PRESCRIBING INFORMATION FOR INSTRUCTIONS ON

ACTIVATION

AFTER MIXING THE PRODUCT REPRESENTS 2000 mL

REFRIGERATED STORAGE IS LIMITED TO 9 DAYS

A SLIGHT YELLOW COLOR DOES NOT ALTER THE QUALITY

AND EFFICACY OF THIS PRODUCT

ASK PHARMACIST ABOUT ADDITIVE COMPATIBILITY

CONTENTS OF EACH 100 mL OF THE
ADMIXED INJECTION

DEXTROSE HYDROUS USP 20 g

ESSENTIAL AMINO ACIDS
LEUCINE 365 mg
ISOLEUCINE 300 mg
VALINE 290 mg
LYSINE (ADDED AS THE
HYDROCHLORIDE SALT) 290 mg
PHENYLALANINE 280 mg
HISTIDINE 240 mg
THREONINE 210 mg
METHIONINE 200 mg
TRYPTOPHAN 90 mg

NONESSENTIAL AMINO ACIDS
ALANINE 1035 mg
ARGININE 575 mg
GLYCINE 515 mg
PROLINE 340 mg
SERINE 250 mg
TYROSINE 20 mg

mEq/L
ACETATE 42
CHLORIDE 20

BALANCED BY IONS FROM AMINO ACIDS
pH ADJUSTED WITH GLACIAL ACETIC ACID

STERILE
SINGLE DOSE CONTAINER

ROOM TEMPERATURE (25°C/77°F)

AVOID EXCESSIVE HEAT

PROTECT FROM FREEZING

SEE PRESCRIBING INFORMATION

Baxter Logo
BAXTER HEALTHCARE CORPORATION
DEERFIELD IL 60015 USA
MADE IN USA

Container Label

EADB9913
NDC 0338-0198-01

1000 mL

CLINIMIX
6/5
SULFITE-FREE
(6% Amino Acid
in 5% Dextrose)
Injection

400 mL INJECTION PORT CHAMBER
12.5% Dextrose Injection USP
600 mL OUTLET PORT CHAMBER
10% Amino Acid Injection
Rx Only

ACTIVATE SEAL AND
MIX THOROUGHTLY BEFORE USE

SEE PRESCRIBING INFORMATION FOR INSTRUCTIONS
ON ACTIVATION
AFTER MIXING THE PRODUCT REPRESENTS 1000 mL
REFRIGERATED STORAGE IS LIMITED TO 9 DAYS
ONCE OVERWRAP IS OPENED
A SLIGHT YELLOW COLOR DOES NOT ALTER THE
QUALITY AND EFFICACY OF THIS PRODUCT
ASK PHARMACIST ABOUT ADDITIVE COMPATIBILITY

CONTENTS OF EACH 100 mL OF THE ADMIXED
INJECTION
DEXTROSE HYDROUS USP 5 g

ESSENTIAL AMINO ACIDS
LEUCINE 438 mg
ISOLEUCINE 360 mg
VALINE 348 mg
LYSINE (ADDED AS THE
HYDROCHLORIDE SALT) 348 mg
PHENYLALANINE 336 mg
HISTIDINE 288 mg
THREONINE 252 mg
METHIONINE 240 mg
TRYPTOPHAN 108 mg

NONESSENTIAL AMINO ACIDS
ALANINE 1242 mg
ARGININE 690 mg
GLYCINE 618 mg
PROLINE 408 mg
SERINE 300 mg
TYROSINE 24 mg

mEq/L
ACETATE 53
CHLORIDE 24

BALANCED BY IONS FROM AMINO ACIDS

pH ADJUSTED WITH GLACIAL ACETIC ACID
AND HYDROCHLORIC ACID

STERILE

SINGLE DOSE CONTAINER

STORE AT ROOM TEMPERATURE (25ºC/77ºF)
IN UNOPENED OVERWRAP

AVOID EXCESSIVE HEAT

PROTECT FROM FREEZING

SEE PRESCRIBING INFORMATION

Baxter Logo
BAXTER HEALTHCARE CORPORATION
DEERFIELD IL 60015 USA
MADE IN BELGIUM

EXP LOT

BE-35-04-040

Container Label

EADP9933
NDC 0338-0188-01

1000 mL

CLINIMIX
8/10
SULFITE-FREE
(8% Amino Acid
in 10% Dextrose)
Injection

360 mL INJECTION PORT CHAMBER
28% Dextrose Injection USP
640 mL OUTLET PORT CHAMBER
12.5% Amino Acid Injection
Rx Only

ACTIVATE SEAL AND
MIX THOROUGHTLY BEFORE USE

SEE PRESCRIBING INFORMATION FOR INSTRUCTIONS
ON ACTIVATION
AFTER MIXING THE PRODUCT REPRESENTS 1000 mL
REFRIGERATED STORAGE IS LIMITED TO 9 DAYS
ONCE OVERWRAP IS OPENED
A SLIGHT YELLOW COLOR DOES NOT ALTER THE
QUALITY AND EFFICACY OF THIS PRODUCT
ASK PHARMACIST ABOUT ADDITIVE COMPATIBILITY

CONTENTS OF EACH 100 mL OF THE ADMIXED
INJECTION
DEXTROSE HYDROUS USP 10 g

ESSENTIAL AMINO ACIDS
LEUCINE 584 mg
ISOLEUCINE 480 mg
VALINE 464 mg
LYSINE (ADDED AS THE
HYDROCHLORIDE SALT) 464 mg
PHENYLALANINE 448 mg
HISTIDINE 384 mg
THREONINE 336 mg
METHIONINE 320 mg
TRYPTOPHAN 144 mg

NONESSENTIAL AMINO ACIDS
ALANINE 1656 mg
ARGININE 920 mg
GLYCINE 824 mg
PROLINE 544 mg
SERINE 400 mg
TYROSINE 32 mg

mEq/L
ACETATE 71
CHLORIDE 32

BALANCED BY IONS FROM AMINO ACIDS
pH ADJUSTED WITH GLACIAL ACETIC ACID
AND HYDROCHLORIC ACID

STERILE

SINGLE DOSE CONTAINER

STORE AT ROOM TEMPERATURE (25ºC/77ºF)
IN UNOPENED OVERWRAP

AVOID EXCESSIVE HEAT

PROTECT FROM FREEZING

SEE PRESCRIBING INFORMATION

Baxter Logo
BAXTER HEALTHCARE CORPORATION
DEERFIELD IL 60015 USA
MADE IN BELGIUM

EXP LOT

BE-35-04-041

Container Label

EADB9935
NDC 0338-0194-01

2000 mL

CLINIMIX
8/10
SULFITE-FREE
(8% Amino Acid
in 10% Dextrose)
Injection

720 mL INJECTION PORT CHAMBER
28% Dextrose Injection USP
1280 mL OUTLET PORT CHAMBER
12.5% Amino Acid Injection
Rx Only

ACTIVATE SEAL AND
MIX THOROUGHTLY BEFORE USE

SEE PRESCRIBING INFORMATION FOR INSTRUCTIONS ON ACTIVATION
AFTER MIXING THE PRODUCT REPRESENTS 2000 mL
REFRIGERATED STORAGE IS LIMITED TO 9 DAYS
ONCE OVERWRAP IS OPENED
A SLIGHT YELLOW COLOR DOES NOT ALTER THE QUALITY AND
EFFICACY OF THIS PRODUCT
ASK PHARMACIST ABOUT ADDITIVE COMPATIBILITY

CONTENTS OF EACH 100 mL OF THE
ADMIXED INJECTION
DEXTROSE HYDROUS USP 10 g

ESSENTIAL AMINO ACIDS
LEUCINE 584 mg
ISOLEUCINE 480 mg
VALINE 464 mg
LYSINE (ADDED AS THE
HYDROCHLORIDE SALT) 464 mg
PHENYLALANINE 448 mg
HISTIDINE 384 mg
THREONINE 336 mg
METHIONINE 320 mg
TRYPTOPHAN 144 mg

NONESSENTIAL AMINO ACIDS
ALANINE 1656 mg
ARGININE 920 mg
GLYCINE 824 mg
PROLINE 544 mg
SERINE 400 mg
TYROSINE 32 mg

mEq/L
ACETATE 71
CHLORIDE 32

BALANCED BY IONS FROM AMINO ACIDS

pH ADJUSTED WITH GLACIAL ACETIC ACID
AND HYDROCHLORIC ACID

STERILE
SINGLE DOSE CONTAINER

STORE AT ROOM TEMPERATURE (25ºC/77ºF)
IN UNOPENED OVERWRAP

AVOID EXCESSIVE HEAT

PROTECT FROM FREEZING

SEE PRESCRIBING INFORMATION

Baxter Logo
BAXTER HEALTHCARE CORPORATION
DEERFIELD IL 60015 USA
MADE IN BELGIUM

Exp Lot

BE-35-04-045

Container Label

EADB9953
NDC 0338-0180-01

1000 mL

CLINIMIX
8/14
SULFITE-FREE
(8% Amino Acid
in 14% Dextrose)
Injection

360 mL INJECTION PORT CHAMBER
39% Dextrose Injection USP
640 mL OUTLET PORT CHAMBER
12.5% Amino Acid Injection
Rx Only

ACTIVATE SEAL AND
MIX THOROUGHTLY BEFORE USE

SEE PRESCRIBING INFORMATION FOR INSTRUCTIONS
ON ACTIVATION
AFTER MIXING THE PRODUCT REPRESENTS 1000 mL
REFRIGERATED STORAGE IS LIMITED TO 9 DAYS
ONCE OVERWRAP IS OPENED
A SLIGHT YELLOW COLOR DOES NOT ALTER THE
QUALITY AND EFFICACY OF THIS PRODUCT
ASK PHARMACIST ABOUT ADDITIVE COMPATIBILITY

CONTENTS OF EACH 100 mL OF THE ADMIXED
INJECTION
DEXTROSE HYDROUS USP 14 g

ESSENTIAL AMINO ACIDS
LEUCINE 584 mg
ISOLEUCINE 480 mg
VALINE 464 mg
LYSINE (ADDED AS THE
HYDROCHLORIDE SALT) 464 mg
PHENYLALANINE 448 mg
HISTIDINE 384 mg
THREONINE 336 mg
METHIONINE 320 mg
TRYPTOPHAN 144 mg

NONESSENTIAL AMINO ACIDS
ALANINE 1656 mg
ARGININE 920 mg
GLYCINE 824 mg
PROLINE 544 mg
SERINE 400 mg
TYROSINE 32 mg

mEq/L
ACETATE 71
CHLORIDE 32

BALANCED BY IONS FROM AMINO ACIDS

pH ADJUSTED WITH GLACIAL ACETIC ACID
AND HYDROCHLORIC ACID

STERILE
SINGLE DOSE CONTAINER

STORE AT ROOM TEMPERATURE (25ºC/77ºF)
IN UNOPENED OVERWRAP

AVOID EXCESSIVE HEAT

PROTECT FROM FREEZING

SEE PRESCRIBING INFORMATION

Baxter Logo
BAXTER HEALTHCARE CORPORATION
DEERFIELD IL 60015 USA
MADE IN BELGIUM

EXP LOT

BE-35-04-043

Container Label

EADB9955
NDC 0338-0184-01

2000 mL

CLINIMIX
8/14
SULFITE-FREE
(8% Amino Acid
in 14% Dextrose)
Injection

720 mL INJECTION PORT CHAMBER
39% Dextrose Injection USP
1280 mL OUTLET PORT CHAMBER
12.5% Amino Acid Injection
Rx Only

ACTIVATE SEAL AND
MIX THOROUGHTLY BEFORE USE

SEE PRESCRIBING INFORMATION FOR INSTRUCTIONS ON ACTIVATION
AFTER MIXING THE PRODUCT REPRESENTS 2000 mL
REFRIGERATED STORAGE IS LIMITED TO 9 DAYS
ONCE OVERWRAP IS OPENED
A SLIGHT YELLOW COLOR DOES NOT ALTER THE QUALITY AND
EFFICACY OF THIS PRODUCT
ASK PHARMACIST ABOUT ADDITIVE COMPATIBILITY

CONTENTS OF EACH 100 mL OF THE
ADMIXED INJECTION
DEXTROSE HYDROUS USP 14 g

ESSENTIAL AMINO ACIDS
LEUCINE 584 mg
ISOLEUCINE 480 mg
VALINE 464 mg
LYSINE (ADDED AS THE
HYDROCHLORIDE SALT) 464 mg
PHENYLALANINE 448 mg
HISTIDINE 384 mg
THREONINE 336 mg
METHIONINE 320 mg
TRYPTOPHAN 144 mg

NONESSENTIAL AMINO ACIDS
ALANINE 1656 mg
ARGININE 920 mg
GLYCINE 824 mg
PROLINE 544 mg
SERINE 400 mg
TYROSINE 32 mg

mEq/L
ACETATE 71
CHLORIDE 32

BALANCED BY IONS FROM AMINO ACIDS

pH ADJUSTED WITH GLACIAL ACETIC ACID
AND HYDROCHLORIC ACID

STERILE
SINGLE DOSE CONTAINER

STORE AT ROOM TEMPERATURE (25ºC/77ºF)
IN UNOPENED OVERWRAP

AVOID EXCESSIVE HEAT

PROTECT FROM FREEZING

SEE PRESCRIBING INFORMATION

Baxter Logo
BAXTER HEALTHCARE CORPORATION
DEERFIELD IL 60015 USA
MADE IN BELGIUM

Exp Lot

BE-35-04-047

Container Label

2B7726L
NDC0338-7001-01

1000 mL

Barcode
(01) 00303387001012

CLINIMIX
4.25/10
SULFITE-FREE
(4.25% Amino Acids in 5% Dextrose)
Injection

500 mL INJECTION PORT CHAMBER
10% Dextrose Injection USP

500 mL OUTLET PORT CHAMBER

8.5% Amino Acid Injection
Rx Only

2D Datamatrix (GS1):
NDC, LOT, EXP

2D Datamatrix
Barcode

ACTIVATE SEAL AND
MIX THOROUGHLY BEFORE USE

SEE PRESCRIBING INFORMATION FOR
INSTRUCTIONS ON ACTIVATION

AFTER MIXING THE PRODUCT
REPRESENTS 1000 mL

REFRIGERATED STORAGE IS LIMITED TO
9 DAYS ONCE OVERWRAP IS OPENED

A SLIGHT YELLOW COLOR DOES NOT
ALTER THE QUALITY AND EFFICACY OF
THIS PRODUCT

ASK PHARMACIST ABOUT ADDITIVE
COMPATIBILITY

CONTENTS OF EACH 100 mL OF THE ADMIXED INJECTION
DEXTROSE HYDROUS USP 5 g

ESSENTIAL AMINO ACIDS
LEUCINE 311 mg
ISOLEUCINE 255 mg
VALINE 247 mg
LYSINE (ADDED AS THE
HYDROCHLORIDE SALT) 247 mg
PHENYLALANINE 238 mg
HISTIDINE 204 mg
THREONINE 179 mg
METHIONINE 170 mg
TRYPTOPHAN 77 mg

NONESSENTIAL AMINO ACIDS
ALANINE 880 mg
ARGININE 489 mg
GLYCINE 438 mg
PROLINE 289 mg
SERINE 213 mg
TYROSINE 17 mg

mEq/L
ACETATE 37
CHLORIDE 17

BALANCED BY IONS FROM AMINO ACIDS
pH ADJUSTED WITH GLACIAL ACETIC ACID
AND HYDROCHLORIC ACID

STERILE
SINGLE DOSE CONTAINER

STORE AT ROOM TEMPERATURE (25°C/77°F)
IN UNOPENED OVERWRAP

AVOID EXCESSIVE HEAT

PROTECT FROM FREEZING

SEE PRESCRIBING INFORMATION

Baxter Logo
BAXTER HEALTHCARE CORPORATION
DEERFIELD IL 60015 USA
MADE IN BELGIUM

1600

1000

800

600

400

200

BE-35-05-077

EXP LOT

Container Label

2B7704L
NDC0338-7003-01

2000mL

Barcode
(01) 00303387003016

CLINIMIX
4.25/5

SULFITE-FREE

(4.25% Amino Acids
in 5% Dextrose)
Injection

1000 mL INJECTION PORT CHAMBER
10% Dextrose Injection USP

1000 mL OUTLET PORT CHAMBER
8.5% Amino Acid Injection

Rx Only

ACTIVATE SEAL AND
MIX THOROUGHLY BEFORE USE

SEE PRESCRIBING INFORMATION FOR INSTRUCTIONS
ON ACTIVATION

AFTER MIXING THE PRODUCT REPRESENTS 2000 mL

REFRIGERATED STORAGE IS LIMITED TO
9 DAYS ONCE OVERWRAP IS OPENED

A SLIGHT YELLOW COLOR DOES NOT ALTER THE
QUALITY AND EFFICACY OF THIS PRODUCT

ASK PHARMACIST ABOUT ADDITIVE COMPATIBILITY

2D Datamatrix (GS1):
NDC, LOT, EXP

2D Datamatrix
Barcode

CONTENTS OF EACH 100 mL OF THE ADMIXED
INJECTION
DEXTROSE HYDROUS USP 5 g

ESSENTIAL AMINO ACIDS
LEUCINE 311 mg
ISOLEUCINE 255 mg
VALINE 247 mg
LYSINE (ADDED AS THE
HYDROCHLORIDE SALT) 247 mg
PHENYLALANINE 238 mg
HISTIDINE 204 mg
THREONINE 179 mg
METHIONINE 170 mg
TRYPTOPHAN 77 mg

NONESSENTIAL AMINO ACIDS
ALANINE 880 mg
ARGININE 489 mg
GLYCINE 438 mg
PROLINE 289 mg
SERINE 213 mg
TYROSINE 17 mg

mEq/L
ACETATE 37
CHLORIDE 17

BALANCED BY IONS FROM AMINO ACIDS
pH ADJUSTED WITH GLACIAL ACETIC ACID
AND HYDROCHLORIC ACID

STERILE
SINGLE DOSE CONTAINER

STORE AT ROOM TEMPERATURE (25°C/77°F)
IN UNOPENED OVERWRAP

AVOID EXCESSIVE HEAT

PROTECT FROM FREEZING

SEE PRESCRIBING INFORMATION

Baxter Logo
BAXTER HEALTHCARE CORPORATION
DEERFIELD IL 60015 USA
MADE IN BELGIUM

2000

1600

1000

800

600

400

200

BE-35-05-073

EXP LOT

Container Label

2B7727L
NDC0338-7005-01

1000mL

Barcode
(01) 00303387005010

CLINIMIX
4.25/10
SULFITE-FREE
(4.25% Amino Acids in 10% Dextrose)
Injection

CENTRAL LINE INFUSION ONLY

500 mL INJECTION PORT CHAMBER
20% Dextrose Injection USP
500 mL OUTLET PORT CHAMBER
8.5% Amino Acid Injection
Rx Only

2D Datamatrix (GS1):
NDC, LOT, EXP

2D Datamatrix
Barcode

ACTIVATE SEAL AND
MIX THOROUGHLY BEFORE USE

SEE PRESCRIBING INFORMATION FOR
INSTRUCTIONS ON ACTIVATION

AFTER MIXING THE PRODUCT
REPRESENTS 1000 mL

REFRIGERATED STORAGE IS LIMITED TO
9 DAYS ONCE OVERWRAP IS OPENED

A SLIGHT YELLOW COLOR DOES NOT
ALTER THE QUALITY AND EFFICACY OF
THIS PRODUCT

ASK PHARMACIST ABOUT ADDITIVE
COMPATIBILITY

CONTENTS OF EACH 100 mL OF THE ADMIXED INJECTION
DEXTROSE HYDROUS USP 10 g

ESSENTIAL AMINO ACIDS
LEUCINE 311 mg
ISOLEUCINE 255 mg
VALINE 247 mg
LYSINE (ADDED AS THE
HYDROCHLORIDE SALT) 247 mg
PHENYLALANINE 238 mg
HISTIDINE 204 mg
THREONINE 179 mg
METHIONINE 170 mg
TRYPTOPHAN 77 mg

NONESSENTIAL AMINO ACIDS
ALANINE 880 mg
ARGININE 489 mg
GLYCINE 438 mg
PROLINE 289 mg
SERINE 213 mg
TYROSINE 17 mg

mEq/L
ACETATE 37
CHLORIDE 17

BALANCED BY IONS FROM AMINO ACIDS
pH ADJUSTED WITH GLACIAL ACETIC ACID
AND HYDROCHLORIC ACID

STERILE
SINGLE DOSE CONTAINER

STORE AT ROOM TEMPERATURE (25°C/77°F)
IN UNOPENED OVERWRAP

AVOID EXCESSIVE HEAT

PROTECT FROM FREEZING

SEE PRESCRIBING INFORMATION

Baxter Logo
BAXTER HEALTHCARE CORPORATION
DEERFIELD IL 60015 USA
MADE IN BELGIUM

1600

1000

800

600

400

200

BE-35-05-078

EXP LOT

Container Label

2B7705L
NDC0338-7007-01

2000mL

Barcode
(01) 00303387007014

CLINIMIX
4.25/10

SULFITE-FREE

(4.25% Amino Acids
in 10% Dextrose)
Injection

CENTRAL LINE INFUSION ONLY

1000 mL INJECTION PORT CHAMBER
20% Dextrose Injection USP

1000 mL OUTLET PORT CHAMBER
8.5% Amino Acid Injection

Rx Only

ACTIVATE SEAL AND
MIX THOROUGHLY BEFORE USE

SEE PRESCRIBING INFORMATION FOR INSTRUCTIONS
ON ACTIVATION

AFTER MIXING THE PRODUCT REPRESENTS 2000 mL

REFRIGERATED STORAGE IS LIMITED TO
9 DAYS ONCE OVERWRAP IS OPENED

A SLIGHT YELLOW COLOR DOES NOT ALTER THE
QUALITY AND EFFICACY OF THIS PRODUCT

ASK PHARMACIST ABOUT ADDITIVE COMPATIBILITY

2D Datamatrix (GS1):
NDC, LOT, EXP

2D Datamatrix
Barcode

CONTENTS OF EACH 100 mL OF THE ADMIXED
INJECTION
DEXTROSE HYDROUS USP 10 g

ESSENTIAL AMINO ACIDS
LEUCINE 311 mg
ISOLEUCINE 255 mg
VALINE 247 mg
LYSINE (ADDED AS THE
HYDROCHLORIDE SALT) 247 mg
PHENYLALANINE 238 mg
HISTIDINE 204 mg
THREONINE 179 mg
METHIONINE 170 mg
TRYPTOPHAN 77 mg

NONESSENTIAL AMINO ACIDS
ALANINE 880 mg
ARGININE 489 mg
GLYCINE 438 mg
PROLINE 289 mg
SERINE 213 mg
TYROSINE 17 mg

mEq/L
ACETATE 37
CHLORIDE 17

BALANCED BY IONS FROM AMINO ACIDS
pH ADJUSTED WITH GLACIAL ACETIC ACID
AND HYDROCHLORIC ACID

STERILE
SINGLE DOSE CONTAINER

STORE AT ROOM TEMPERATURE (25°C/77°F)
IN UNOPENED OVERWRAP

AVOID EXCESSIVE HEAT

PROTECT FROM FREEZING

SEE PRESCRIBING INFORMATION

Baxter Logo
BAXTER HEALTHCARE CORPORATION
DEERFIELD IL 60015 USA
MADE IN BELGIUM

2000

1600

1000

800

600

400

200

BE-35-05-074

EXP LOT

Container Label

2B7730L
NDC0338-7009-01

1000mL

Barcode
(01) 00303387009018

CLINIMIX
5/15
SULFITE-FREE
(5% Amino Acids
in 15% Dextrose)
Injection

CENTRAL LINE INFUSION ONLY

500 mL INJECTION PORT CHAMBER
30% Dextrose Injection USP
500 mL OUTLET PORT CHAMBER
10% Amino Acid Injection
Rx Only

2D Datamatrix (GS1):
NDC, LOT, EXP

2D Datamatrix
Barcode

ACTIVATE SEAL AND
MIX THOROUGHLY BEFORE USE

SEE PRESCRIBING INFORMATION FOR
INSTRUCTIONS ON ACTIVATION

AFTER MIXING THE PRODUCT
REPRESENTS 1000 mL

REFRIGERATED STORAGE IS LIMITED TO
9 DAYS ONCE OVERWRAP IS OPENED

A SLIGHT YELLOW COLOR DOES NOT
ALTER THE QUALITY AND EFFICACY OF
THIS PRODUCT

ASK PHARMACIST ABOUT ADDITIVE
COMPATIBILITY

CONTENTS OF EACH 100 mL OF THE ADMIXED INJECTION
DEXTROSE HYDROUS USP 15 g

ESSENTIAL AMINO ACIDS
LEUCINE 365 mg
ISOLEUCINE 300 mg
VALINE 290 mg
LYSINE (ADDED AS THE
HYDROCHLORIDE SALT) 290 mg
PHENYLALANINE 280 mg
HISTIDINE 240 mg
THREONINE 210 mg
METHIONINE 200 mg
TRYPTOPHAN 90 mg

NONESSENTIAL AMINO ACIDS
ALANINE 1035 mg
ARGININE 575 mg
GLYCINE 515 mg
PROLINE 340 mg
SERINE 250 mg
TYROSINE 20 mg

mEq/L
ACETATE 42
CHLORIDE 20

BALANCED BY IONS FROM AMINO ACIDS
pH ADJUSTED WITH GLACIAL ACETIC ACID
AND HYDROCHLORIC ACID

STERILE
SINGLE DOSE CONTAINER

STORE AT ROOM TEMPERATURE (25°C/77°F)
IN UNOPENED OVERWRAP

AVOID EXCESSIVE HEAT

PROTECT FROM FREEZING

SEE PRESCRIBING INFORMATION

Baxter Logo
BAXTER HEALTHCARE CORPORATION
DEERFIELD IL 60015 USA
MADE IN BELGIUM

1600

1000

800

600

400

200

BE-35-05-079

EXP LOT

Container Label

2B7709L
NDC0338-7011-01

2000mL

Barcode
(01) 00303387011011

CLINIMIX
5/15

SULFITE-FREE

(5% Amino Acids
in 15% Dextrose)
Injection

CENTRAL LINE INFUSION ONLY

1000 mL INJECTION PORT CHAMBER
30% Dextrose Injection USP

1000 mL OUTLET PORT CHAMBER
10% Amino Acid Injection

Rx Only

ACTIVATE SEAL AND
MIX THOROUGHLY BEFORE USE

SEE PRESCRIBING INFORMATION FOR INSTRUCTIONS
ON ACTIVATION

AFTER MIXING THE PRODUCT REPRESENTS 2000 mL

REFRIGERATED STORAGE IS LIMITED TO
9 DAYS ONCE OVERWRAP IS OPENED

A SLIGHT YELLOW COLOR DOES NOT ALTER THE
QUALITY AND EFFICACY OF THIS PRODUCT

ASK PHARMACIST ABOUT ADDITIVE COMPATIBILITY

2D Datamatrix (GS1):
NDC, LOT, EXP

2D Datamatrix
Barcode

CONTENTS OF EACH 100 mL OF THE ADMIXED
INJECTION
DEXTROSE HYDROUS USP 15 g

ESSENTIAL AMINO ACIDS
LEUCINE 365 mg
ISOLEUCINE 300 mg
VALINE 290 mg
LYSINE (ADDED AS THE
HYDROCHLORIDE SALT) 290 mg
PHENYLALANINE 280 mg
HISTIDINE 240 mg
THREONINE 210 mg
METHIONINE 200 mg
TRYPTOPHAN 90 mg

NONESSENTIAL AMINO ACIDS
ALANINE 1035 mg
ARGININE 575 mg
GLYCINE 515 mg
PROLINE 340 mg
SERINE 250 mg
TYROSINE 20 mg

mEq/L
ACETATE 42
CHLORIDE 20

BALANCED BY IONS FROM AMINO ACIDS
pH ADJUSTED WITH GLACIAL ACETIC ACID
AND HYDROCHLORIC ACID

STERILE
SINGLE DOSE CONTAINER

STORE AT ROOM TEMPERATURE (25°C/77°F)
IN UNOPENED OVERWRAP

AVOID EXCESSIVE HEAT

PROTECT FROM FREEZING

SEE PRESCRIBING INFORMATION

Baxter Logo
BAXTER HEALTHCARE CORPORATION
DEERFIELD IL 60015 USA
MADE IN BELGIUM

2000

1600

1000

800

600

400

200

BE-35-05-075

EXP LOT

Container Label

2B7731L
NDC0338-7013-01

1000mL

Barcode
(01) 00303387013015

CLINIMIX
5/20
SULFITE-FREE
(5% Amino Acids
in 20% Dextrose)
Injection

CENTRAL LINE INFUSION ONLY

500 mL INJECTION PORT CHAMBER
40% Dextrose Injection USP
500 mL OUTLET PORT CHAMBER
10% Amino Acid Injection
Rx Only

2D Datamatrix (GS1):
NDC, LOT, EXP

2D Datamatrix
Barcode

ACTIVATE SEAL AND
MIX THOROUGHLY BEFORE USE

SEE PRESCRIBING INFORMATION FOR
INSTRUCTIONS ON ACTIVATION

AFTER MIXING THE PRODUCT
REPRESENTS 1000 mL

REFRIGERATED STORAGE IS LIMITED TO
9 DAYS ONCE OVERWRAP IS OPENED

A SLIGHT YELLOW COLOR DOES NOT
ALTER THE QUALITY AND EFFICACY OF
THIS PRODUCT

ASK PHARMACIST ABOUT ADDITIVE
COMPATIBILITY

CONTENTS OF EACH 100 mL OF THE ADMIXED INJECTION
DEXTROSE HYDROUS USP 20 g

ESSENTIAL AMINO ACIDS
LEUCINE 365 mg
ISOLEUCINE 300 mg
VALINE 290 mg
LYSINE (ADDED AS THE
HYDROCHLORIDE SALT) 290 mg
PHENYLALANINE 280 mg
HISTIDINE 240 mg
THREONINE 210 mg
METHIONINE 200 mg
TRYPTOPHAN 90 mg

NONESSENTIAL AMINO ACIDS
ALANINE 1035 mg
ARGININE 575 mg
GLYCINE 515 mg
PROLINE 340 mg
SERINE 250 mg
TYROSINE 20 mg

mEq/L
ACETATE 42
CHLORIDE 20

BALANCED BY IONS FROM AMINO ACIDS
pH ADJUSTED WITH GLACIAL ACETIC ACID
AND HYDROCHLORIC ACID

STERILE
SINGLE DOSE CONTAINER

STORE AT ROOM TEMPERATURE (25°C/77°F)
IN UNOPENED OVERWRAP

AVOID EXCESSIVE HEAT

PROTECT FROM FREEZING

SEE PRESCRIBING INFORMATION

Baxter Logo
BAXTER HEALTHCARE CORPORATION
DEERFIELD IL 60015 USA
MADE IN BELGIUM

1600

1000

800

600

400

200

BE-35-04-996

EXP LOT

Container Label

2B7710L
NDC0338-7015-01

2000mL

Barcode
(01) 00303387015019

CLINIMIX
5/20

SULFITE-FREE

(5% Amino Acids
in 20% Dextrose)
Injection

CENTRAL LINE INFUSION ONLY

1000 mL INJECTION PORT CHAMBER
40% Dextrose Injection USP

1000 mL OUTLET PORT CHAMBER
10% Amino Acid Injection

Rx Only

ACTIVATE SEAL AND
MIX THOROUGHLY BEFORE USE

SEE PRESCRIBING INFORMATION FOR INSTRUCTIONS ON
ACTIVATION

AFTER MIXING THE PRODUCT REPRESENTS 2000 mL

REFRIGERATED STORAGE IS LIMITED
TO 9 DAYS ONCE OVERWRAP IS OPENED

A SLIGHT YELLOW COLOR DOES NOT ALTER THE
QUALITY AND EFFICACY OF THIS PRODUCT

ASK PHARMACIST ABOUT ADDITIVE COMPATIBILITY

2D Datamatrix (GS1):
NDC, LOT, EXP

2D Datamatrix
Barcode

CONTENTS OF EACH 100 mL OF THE ADMIXED
INJECTION
DEXTROSE HYDROUS USP 20 g

ESSENTIAL AMINO ACIDS
LEUCINE 365 mg
ISOLEUCINE 300 mg
VALINE 290 mg
LYSINE (ADDED AS THE
HYDROCHLORIDE SALT) 290 mg
PHENYLALANINE 280 mg
HISTIDINE 240 mg
THREONINE 210 mg
METHIONINE 200 mg
TRYPTOPHAN 90 mg

NONESSENTIAL AMINO ACIDS
ALANINE 1035 mg
ARGININE 575 mg
GLYCINE 515 mg
PROLINE 340 mg
SERINE 250 mg
TYROSINE 20 mg

mEq/L
ACETATE 42
CHLORIDE 20

BALANCED BY IONS FROM AMINO ACIDS
pH ADJUSTED WITH GLACIAL ACETIC ACID
AND HYDROCHLORIC ACID

STERILE
SINGLE DOSE CONTAINER

STORE AT ROOM TEMPERATURE (25°C/77°F)
IN UNOPENED OVERWRAP

AVOID EXCESSIVE HEAT

PROTECT FROM FREEZING

SEE PRESCRIBING INFORMATION

Baxter Logo
BAXTER HEALTHCARE CORPORATION
DEERFIELD IL 60015 USA
MADE IN BELGIUM

2000

1600

1000

800

600

400

200

BE-35-04-988

EXP LOT